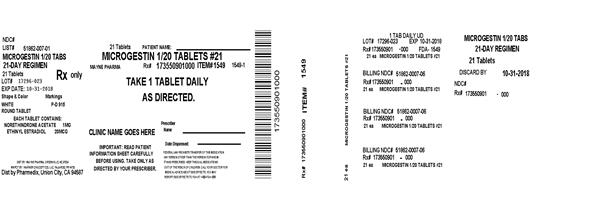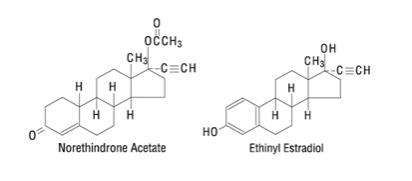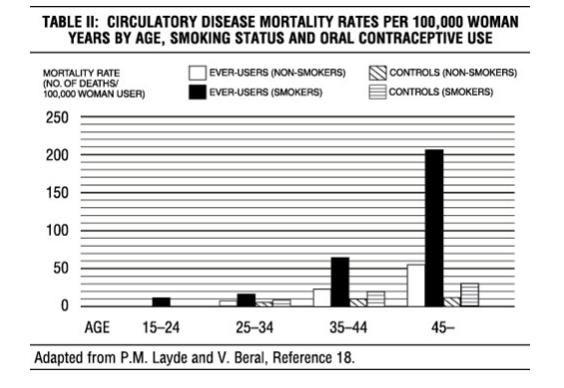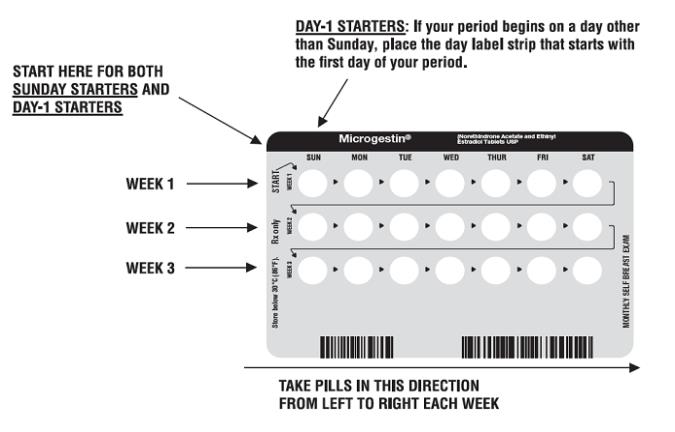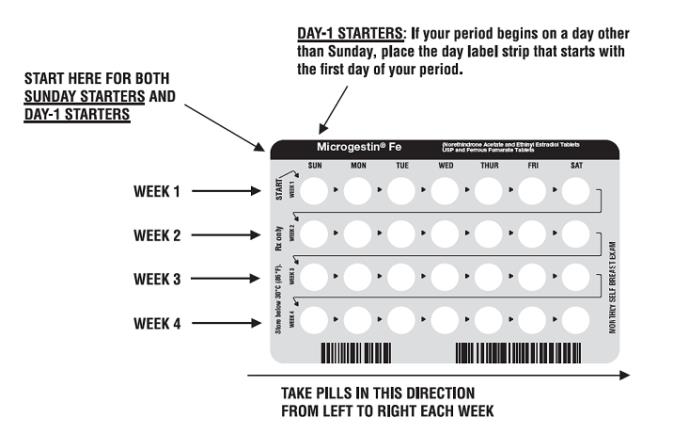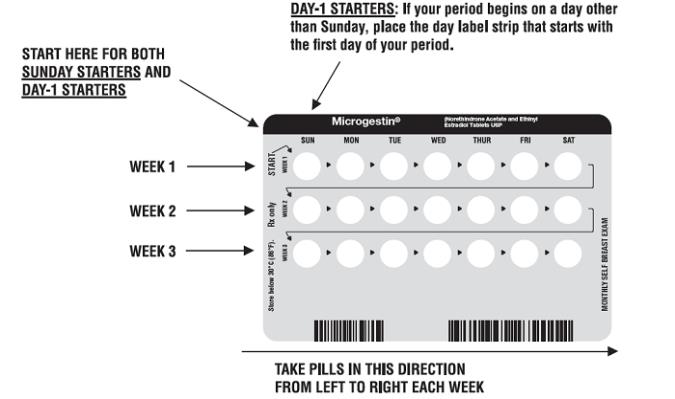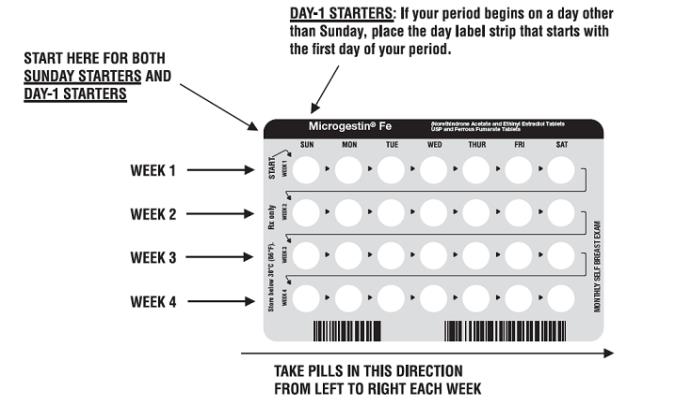 DRUG LABEL: MICROGESTIN 1/20
NDC: 53002-1549 | Form: TABLET
Manufacturer: RPK Pharmaceuticals, Inc.
Category: prescription | Type: HUMAN PRESCRIPTION DRUG LABEL
Date: 20201215

ACTIVE INGREDIENTS: NORETHINDRONE ACETATE 1 mg/1 1; ETHINYL ESTRADIOL 20 ug/1 1
INACTIVE INGREDIENTS: ACACIA; LACTOSE, UNSPECIFIED FORM; MAGNESIUM STEARATE; STARCH, CORN; SUCROSE; TALC

MICROGESTIN®
(Norethindrone Acetate and Ethinyl Estradiol Tablets, USP)

MICROGESTIN®
(Norethindrone Acetate and Ethinyl Estradiol Tablets, USP)

MICROGESTIN® 1/20
(Each white tablet contains 1 mg norethindrone acetate and 20 mcg ethinyl estradiol.)
MICROGESTIN® 1.5/30
(Each green tablet contains 1.5 mg norethindrone acetate and 30 mcg ethinyl estradiol.)

MICROGESTIN® Fe
(Norethindrone Acetate and Ethinyl Estradiol Tablets, USP and Ferrous Fumarate Tablets*)
*Ferrous fumarate tablets are not USP for dissolution and assay.

MICROGESTIN® Fe 1/20
(Each white tablet contains 1 mg norethindrone acetate and 20 mcg ethinyl estradiol. Each brown tablet contains 75 mg ferrous fumarate.)

MICROGESTIN® Fe 1.5/30
(Each green tablet contains 1.5 mg norethindrone acetate and 30 mcg ethinyl estradiol. Each brown tablet contains 75 mg ferrous fumarate.)

Patients should be counseled that this product does not protect against HIV infection (AIDS) and other sexually transmitted diseases.

DESCRIPTION

MICROGESTIN and MICROGESTIN Fe are progestogen-estrogen combinations.

MICROGESTIN Fe 1/20 and 1.5/30: Each provides a continuous dosage regimen consisting of 21 oral contraceptive tablets and seven ferrous fumarate tablets. The ferrous fumarate tablets are present to facilitate ease of drug administration via a 28-day regimen, are non-hormonal, and do not serve any therapeutic purpose.

Each white tablet contains norethindrone acetate (17 alpha-ethinyl-19-nortestosterone acetate), 1 mg; ethinyl estradiol (17 alpha-ethinyl-1,3,5(10)-estratriene-3, 17 beta-diol), 20 mcg. Also contains acacia, NF; lactose, NF; magnesium stearate, NF; starch, NF; confectioner’s sugar, NF; talc, USP.

Each green tablet contains norethindrone acetate (17 alpha-ethinyl-19-nortestosterone acetate), 1.5 mg; ethinyl estradiol (17 alpha-ethinyl-1,3,5(10)-estratriene-3, 17 beta-diol), 30 mcg. Also contains acacia, NF; lactose, NF; magnesium stearate, NF; starch, NF; confectioner’s sugar, NF; talc, USP; D&C yellow No. 10; FD&C yellow No. 6; FD&C blue No. 1.

The structural formulas are as follows:

Each brown tablet contains ferrous fumarate, USP; mannitol, USP; povidone, USP; microcrystalline cellulose, NF; sodium starch glycolate, NF; magnesium stearate, NF; sucralose, NF; spearmint flavor.

CLINICAL PHARMACOLOGY

Combination oral contraceptives act by suppression of gonadotropins. Although the primary mechanism of this action is inhibition of ovulation, other alterations include changes in the cervical mucus (which increase the difficulty of sperm entry into the uterus) and the endometrium (which reduce the likelihood of implantation).

Pharmacokinetics

The pharmacokinetics of MICROGESTIN have not been characterized; however, the following pharmacokinetic information regarding norethindrone acetate and ethinyl estradiol is taken from the literature.

Absorption

Norethindrone acetate appears to be completely and rapidly deacetylated to norethindrone after oral administration, since the disposition of norethindrone acetate is indistinguishable from that of orally administered norethindrone (1). Norethindrone acetate and ethinyl estradiol are subject to first-pass metabolism after oral dosing, resulting in an absolute bioavailability of approximately 64% for norethindrone and 43% for ethinyl estradiol (1-3).

Distribution

Volume of distribution of norethindrone and ethinyl estradiol ranges from 2 to 4 L/kg (1-3). Plasma protein binding of both steroids is extensive (greater than 95%); norethindrone binds to both albumin and sex hormone binding globulin, whereas ethinyl estradiol binds only to albumin (4).

Metabolism

Norethindrone undergoes extensive biotransformation, primarily via reduction, followed by sulfate and glucuronide conjugation. The majority of metabolites in the circulation are sulfates, with glucuronides accounting for most of the urinary metabolites (5). A small amount of norethindrone acetate is metabolically converted to ethinyl estradiol. Ethinyl estradiol is also extensively metabolized, both by oxidation and by conjugation with sulfate and glucuronide. Sulfates are the major circulating conjugates of ethinyl estradiol and glucuronides predominate in urine. The primary oxidative metabolite is 2-hydroxy ethinyl estradiol, formed by the CYP3A4 isoform of cytochrome P450. Part of the first-pass metabolism of ethinyl estradiol is believed to occur in gastrointestinal mucosa. Ethinyl estradiol may undergo enterohepatic circulation (6).

Excretion

Norethindrone and ethinyl estradiol are excreted in both urine and feces, primarily as metabolites (5,6). Plasma clearance values for norethindrone and ethinyl estradiol are similar (approximately 0.4 L/hr/kg) (1-3).

Special Population

Race:
The effect of race on the disposition of MICROGESTIN has not been evaluated.

Renal Insufficiency

The effect of renal disease on the disposition of MICROGESTIN has not been evaluated. In premenopausal women with chronic renal failure undergoing peritoneal dialysis who received multiple doses of an oral contraceptive containing ethinyl estradiol and norethindrone, plasma ethinyl estradiol concentrations were higher and norethindrone concentrations were unchanged compared to concentrations in premenopausal women with normal renal function.

Hepatic Insufficiency

The effect of hepatic disease on the disposition of MICROGESTIN has not been evaluated. However, ethinyl estradiol and norethindrone may be poorly metabolized in patients with impaired liver function.

Drug-Drug Interactions

Numerous drug-drug interactions have been reported for oral contraceptives. A summary of these is found under PRECAUTIONS, Drug Interactions.

INDICATIONS AND USAGE

MICROGESTIN and MICROGESTIN Fe are indicated for the prevention of pregnancy in women who elect to use oral contraceptives as a method of contraception.

Oral contraceptives are highly effective. Table I lists the typical accidental pregnancy rates for users of combination oral contraceptives and other methods of contraception. The efficacy of these contraceptive methods, except sterilization, depends upon the reliability with which they are used. Correct and consistent use of methods can result in lower failure rates.

TABLE I:
LOWEST EXPECTED AND TYPICAL FAILURE RATES DURING THE FIRST YEAR OF CONTINUOUS USE OF A METHOD

% Of Women Experiencing an Unintended Pregnancy in the First Year of Continuous Use
 | Lowest
Method | Expected* | Typical**
(No contraception) ...................... | (85) | (85)
Oral contraceptives .................... |  | 3
combined ................................ | 0.1 | N/A***
progestin only ........................ | 0.5 | N/A***
Diaphragm with spermicidal cream or jelly .......................... | 6 | 20
Spermicides alone (foam, creams, gels, vaginal suppositories, and vaginal film) ................................ | 6 | 26
Vaginal Sponge
nulliparous .............................. | 9 | 20
parous .................................... | 20 | 40
Implant........................................ | 0.05 | 0.05
Injection: depot medroxyprogesterone acetate ...................... | 0.3 | 0.3
IUD
progesterone T ........................ | 1.5 | 2.0
copper T 380A ........................ | 0.6 | 0.8
LNg 20 .................................... | 0.1 | 0.1
Condom without spermicides
female...................................... | 5 | 21
male ........................................ | 3 | 14
Cervical Cap with spermicidal cream or jelly
nulliparous .............................. | 9 | 20
parous .................................... | 26 | 40
Periodic abstinence (all methods) .............................. | 1-9 | 25
Withdrawal.................................. | 4 | 19
Female sterilization...................... | 0.5 | 0.5
Male sterilization ........................ | 0.10 | 0.15
Adapted from RA Hatcher et al, Reference 7.
*The authors’ best guess of the percentage of women expected to experience an accidental pregnancy among couples who initiate a method (not necessarily for the first time) and who use it consistently and correctly during the first year if they do not stop for any other reason.
**This term represents “typical” couples who initiate use of a method (not necessarily for the first time), who experience an accidental pregnancy during the first year if they do not stop use for any other reason.
***N/A - Data not available.

CONTRAINDICATIONS

Oral contraceptives should not be used in women who currently have the following conditions:

- Thrombophlebitis or thromboembolic disorders
- A past history of deep vein thrombophlebitis or thromboembolic disorders
- Cerebral vascular or coronary artery disease
- Known or suspected carcinoma of the breast
- Carcinoma of the endometrium or other known or suspected estrogen-dependent neoplasia
- Undiagnosed abnormal genital bleeding
- Cholestatic jaundice of pregnancy or jaundice with prior pill use
- Hepatic adenomas or carcinomas
- Known or suspected pregnancy
- Are receiving Hepatitis C drug combination containing ombitasvir/paritaprevir/ritonavir, with or without dasabuvir, due to the potential for ALT elevations (see Warnings, RISK OF LIVER ENZYME ELEVATIONS WITH CONCOMITANT HEPATITIS C TREATMENT).

WARNINGS

Cigarette smoking increases the risk of serious cardiovascular side effects from oral contraceptive use. This risk increases with age and with heavy smoking (15 or more cigarettes per day) and is quite marked in women over 35 years of age. Women who use oral contraceptives should be strongly advised not to smoke.

The use of oral contraceptives is associated with increased risks of several serious conditions including myocardial infarction, thromboembolism, stroke, hepatic neoplasia, and gallbladder disease, although the risk of serious morbidity or mortality is very small in healthy women without underlying risk factors. The risk of morbidity and mortality increases significantly in the presence of other underlying risk factors such as hypertension, hyperlipidemias, obesity, and diabetes.

Practitioners prescribing oral contraceptives should be familiar with the following information relating to these risks.

The information contained in this package insert is principally based on studies carried out in patients who used oral contraceptives with higher formulations of estrogens and progestogens than those in common use today. The effect of long-term use of the oral contraceptives with lower formulations of both estrogens and progestogens remains to be determined.

Throughout this labeling, epidemiological studies reported are of two types: retrospective or case control studies and prospective or cohort studies. Case control studies provide a measure of the relative risk of a disease, namely, a ratio of the incidence of a disease among oral contraceptive users to that among nonusers. The relative risk does not provide information on the actual clinical occurrence of a disease. Cohort studies provide a measure of attributable risk, which is the difference in the incidence of disease between oral contraceptive users and nonusers. The attributable risk does provide information about the actual occurrence of a disease in the population (adapted from References 8 and 9 with the author’s permission). For further information, the reader is referred to a text on epidemiological methods.

1. Thromboembolic Disorders and Other Vascular Problems

a. Myocardial infarction

An increased risk of myocardial infarction has been attributed to oral contraceptive use. This risk is primarily in smokers or women with other underlying risk factors for coronary artery disease such as hypertension, hypercholesterolemia, morbid obesity, and diabetes. The relative risk of heart attack for current oral contraceptive users has been estimated to be two to six (10-16). The risk is very low under the age of 30.

Smoking in combination with oral contraceptive use has been shown to contribute substantially to the incidence of myocardial infarctions in women in their mid-thirties or older with smoking accounting for the majority of excess cases (17). Mortality rates associated with circulatory disease have been shown to increase substantially in smokers over the age of 35 and non-smokers over the age of 40 (Table II) among women who use oral contraceptives.

Oral contraceptives may compound the effects of well-known risk factors, such as hypertension, diabetes, hyperlipidemias, age and obesity (19). In particular, some progestogens are known to decrease HDL cholesterol and cause glucose intolerance, while estrogens may create a state of hyperinsulinism (20-24). Oral contraceptives have been shown to increase blood pressure among users (see section 9 in WARNINGS). Similar effects on risk factors have been associated with an increased risk of heart disease. Oral contraceptives must be used with caution in women with cardiovascular disease risk factors.

b. Thromboembolism

An increased risk of thromboembolic and thrombotic disease associated with the use of oral contraceptives is well established. Case control studies have found the relative risk of users compared to non-users to be 3 for the first episode of superficial venous thrombosis, 4 to 11 for deep vein thrombosis or pulmonary embolism, and 1.5 to 6 for women with predisposing conditions for venous thromboembolic disease (9, 10, 25-30). Cohort studies have shown the relative risk to be somewhat lower, about 3 for new cases and about 4.5 for new cases requiring hospitalization (31). The risk of thromboembolic disease due to oral contraceptives is not related to length of use and disappears after pill use is stopped (8).

A two- to four-fold increase in relative risk of postoperative thromboembolic complications has been reported with the use of oral contraceptives (15,32). The relative risk of venous thrombosis in women who have predisposing conditions is twice that of women without such medical conditions (15,32). If feasible, oral contraceptives should be discontinued at least four weeks prior to and for two weeks after elective surgery of a type associated with an increase in risk of thromboembolism and during and following prolonged immobilization. Since the immediate postpartum period is also associated with an increased risk of thromboembolism, oral contraceptives should be started no earlier than four to six weeks after delivery in women who elect not to breastfeed.

c. Cerebrovascular disease

Oral contraceptives have been shown to increase both the relative and attributable risks of cerebrovascular events (thrombotic and hemorrhagic strokes), although, in general, the risk is greatest among older (greater than 35 years), hypertensive women who also smoke. Hypertension was found to be a risk factor for both users and nonusers, for both types of strokes, while smoking interacted to increase the risk for hemorrhagic strokes (33-35).

In a large study, the relative risk of thrombotic strokes has been shown to range from 3 for normotensive users to 14 for users with severe hypertension (36). The relative risk of hemorrhagic stroke is reported to be 1.2 for non-smokers who used oral contraceptives, 2.6 for smokers who did not use oral contraceptives, 7.6 for smokers who used oral contraceptives, 1.8 for normotensive users, and 25.7 for users with severe hypertension (36). The attributable risk is also greater in older women (9).

d. Dose-related risk of vascular disease from oral contraceptives.

A positive association has been observed between the amount of estrogen and progestogen in oral contraceptives and the risk of vascular disease (37-39). A decline in serum high-density lipoproteins (HDL) has been reported with many progestational agents (20-22). A decline in serum high-density lipoproteins has been associated with an increased incidence of ischemic heart disease. Because estrogens increase HDL cholesterol, the net effect of an oral contraceptive depends on a balance achieved between doses of estrogen and progestin and the nature of the progestin used in the contraceptives. The amount and activity of both hormones should be considered in the choice of an oral contraceptive.

Minimizing exposure to estrogen and progestogen is in keeping with good principles of therapeutics. For any particular oral contraceptive, the dosage regimen prescribed should be one which contains the least amount of estrogen and progestogen that is compatible with the needs of the individual patient. New acceptors of oral contraceptive agents should be started on preparations containing the lowest dose of estrogen which produces satisfactory results for the patient.

e. Persistence of risk of vascular disease

There are two studies which have shown persistence of risk of vascular disease for ever-users of oral contraceptives. In a study in the United States, the risk of developing myocardial infarction after discontinuing oral contraceptives persists for at least 9 years for women 40-49 years who had used oral contraceptives for 5 or more years, but this increased risk was not demonstrated in other age groups (14). In another study in Great Britain, the risk of developing cerebrovascular disease persisted for at least 6 years after discontinuation of oral contraceptives, although excess risk was very small (40). However, both studies were performed with oral contraceptive formulations containing 50 mcg or higher of estrogens.

2. Estimates of Mortality from Contraceptive Use

One study gathered data from a variety of sources which have estimated the mortality rate associated with different methods of contraception at different ages (Table III). These estimates include the combined risk of death associated with contraceptive methods plus the risk attributable to pregnancy in the event of method failure. Each method of contraception has its specific benefits and risks. The study concluded that with the exception of oral contraceptive users 35 and older who smoke and 40 and older who do not smoke, mortality associated with all methods of birth control is low and below that associated with childbirth. The observation of a possible increase in risk of mortality with age for oral contraceptive users is based on data gathered in the 1970’s but not reported until 1983 (41). However, current clinical practice involves the use of lower estrogen dose formulations combined with careful restriction of oral contraceptive use to women who do not have the various risk factors listed in this labeling.

Because of these changes in practice and, also, because of some limited new data which suggest that the risk of cardiovascular disease with the use of oral contraceptives may now be less than previously observed (Porter JB, Hunter J, Jick H, et al. Oral contraceptives and nonfatal vascular disease. Obstet Gynecol 1985;66:1-4; and Porter JB, Hershel J, Walker AM. Mortality among oral contraceptive users. Obstet Gynecol 1987;70:29-32), the Fertility and Maternal Health Drugs Advisory Committee was asked to review the topic in 1989. The Committee concluded that although cardiovascular disease risks may be increased with oral contraceptive use after age 40 in healthy non-smoking women (even with the newer low-dose formulations), there are greater potential health risks associated with pregnancy in older women and with the alternative surgical and medical procedures which may be necessary if such women do not have access to effective and acceptable means of contraception.

Therefore, the Committee recommended that the benefits of oral contraceptive use by healthy non-smoking women over 40 may outweigh the possible risks. Of course, older women, as all women who take oral contraceptives, should take the lowest possible dose formulation that is effective.

TABLE III:
ANNUAL NUMBER OF BIRTH-RELATED OR METHOD-RELATED DEATHS ASSOCIATED WITH CONTROL OF FERTILITY PER 100,000 NONSTERILE WOMEN BY FERTILITY CONTROL METHOD ACCORDING TO AGE

Method of control and outcome | 15-19 | 20-24 | 25-29 | 30-34 | 35-39 | 40-44
No fertility control methods | 7.0 | 7.4 | 9.1 | 14.8 | 25.7 | 28.2
Oral contraceptives non-smoker** | 0.3 | 0.5 | 0.9 | 1.9 | 13.8 | 31.6
Oral contraceptives smoker** | 2.2 | 3.4 | 6.6 | 13.5 | 51.1 | 117.2
IUD** | 0.8 | 0.8 | 1.0 | 1.0 | 1.4 | 1.4
Condom* | 1.1 | 1.6 | 0.7 | 0.2 | 0.3 | 0.4
Diaphragm/spermicide* | 1.9 | 1.2 | 1.2 | 1.3 | 2.2 | 2.8
Periodic abstinence* | 2.5 | 1.6 | 1.6 | 1.7 | 2.9 | 3.6
*Deaths are birth related.
**Deaths are method related.
Adapted from H.W. Ory, Reference 41.

3. Carcinoma of the Reproductive Organs

Numerous epidemiological studies have been performed on the incidence of breast, endometrial, ovarian, and cervical cancer in women using oral contraceptives. Most of the studies on breast cancer and oral contraceptive use report that the use of oral contraceptives is not associated with an increase in the risk of developing breast cancer (42,44,89). Some studies have reported an increased risk of developing breast cancer in certain subgroups of oral contraceptive users, but the findings reported in these studies are not consistent (43,45-49,85-88).

Some studies suggest that oral contraceptive use has been associated with an increase in the risk of cervical intraepithelial neoplasia in some populations of women (51-54). However, there continues to be controversy about the extent to which such findings may be due to differences in sexual behavior and other factors.

In spite of many studies of the relationship between oral contraceptive use and breast and cervical cancers, a cause and effect relationship has not been established.

4. Hepatic Neoplasia

Benign hepatic adenomas are associated with oral contraceptive use, although the incidence of benign tumors is rare in the United States. Indirect calculations have estimated the attributable risk to be in the range of 3.3 cases/100,000 for users, a risk that increases after four or more years of use (55).Rupture of rare, benign, hepatic adenomas may cause death through intra-abdominal hemorrhage (56,57).

Studies from Britain have shown an increased risk of developing hepatocellular carcinoma (58-60) in long-term (greater than 8 years) oral contraceptive users. However, these cancers are extremely rare in the U.S., and the attributable risk (the excess incidence) of liver cancers in oral contraceptive users approaches less than one per million users.

5. Risk of Liver Enzyme Elevations with Concomitant Hepatitis C Treatment

During clinical trials with the Hepatitis C combination drug regimen that contains ombitasvir/paritaprevir/ritonavir, with or without dasabuvir, ALT elevations greater than 5 times the upper limit of normal (ULN), including some cases greater than 20 times the ULN, were significantly more frequent in women using ethinyl estradiol-containing medications such as COCs. Discontinue MICROGESTIN and MICROGESTIN Fe prior to starting therapy with the combination regimen ombitasvir/paritaprevir/ritonavir, with or without dasabuvir [see Contraindications (4)]. MICROGESTIN and MICROGESTIN Fe can be restarted approximately 2 weeks following completion of treatment with the combination drug regimen.

6. Ocular Lesions

There have been clinical case reports of retinal thrombosis associated with the use of oral contraceptives. Oral contraceptives should be discontinued if there is unexplained partial or complete loss of vision; onset of proptosis or diplopia; papilledema; or retinal vascular lesions. Appropriate diagnostic and therapeutic measures should be undertaken immediately.

7. Oral Contraceptive Use Before and During Early Pregnancy

Extensive epidemiological studies have revealed no increased risk of birth defects in women who have used oral contraceptives prior to pregnancy (61-63). Studies also do not suggest a teratogenic effect, particularly insofar as cardiac anomalies and limb reduction defects are concerned (61,62,64,65), when taken inadvertently during early pregnancy.

The administration of oral contraceptives to induce withdrawal bleeding should not be used as a test for pregnancy. Oral contraceptives should not be used during pregnancy to treat threatened or habitual abortion.

It is recommended that for any patient who has missed two consecutive periods, pregnancy should be ruled out before continuing oral contraceptive use. If the patient has not adhered to the prescribed schedule, the possibility of pregnancy should be considered at the time of the first missed period. Oral contraceptive use should be discontinued if pregnancy is confirmed.

8. Gallbladder Disease

Earlier studies have reported an increased lifetime relative risk of gallbladder surgery in users of oral contraceptives and estrogens (66,67). More recent studies, however, have shown that the relative risk of developing gallbladder disease among oral contraceptive users may be minimal (68-70). The recent findings of minimal risk may be related to the use of oral contraceptive formulations containing lower hormonal doses of estrogens and progestogens.

9. Carbohydrate And Lipid Metabolic Effects

Oral contraceptives have been shown to cause glucose intolerance in a significant percentage of users (23). Oral contraceptives containing greater than 75 mcg of estrogens cause hyperinsulinism, while lower doses of estrogen cause less glucose intolerance (71). Progestogens increase insulin secretion and create insulin resistance, this effect varying with different progestational agents (23,72). However, in the non-diabetic woman, oral contraceptives appear to have no effect on fasting blood glucose (73). Because of these demonstrated effects, prediabetic and diabetic women should be carefully observed while taking oral contraceptives.

A small proportion of women will have persistent hypertriglyceridemia while on the pill. As discussed earlier (see WARNINGS 1a. and 1d.), changes in serum triglycerides and lipoprotein levels have been reported in oral contraceptive users.

10. Elevated Blood Pressure

An increase in blood pressure has been reported in women taking oral contraceptives (74) and this increase is more likely in older oral contraceptive users (75) and with continued use (74). Data from the Royal College of General Practitioners (18) and subsequent randomized trials have shown that the incidence of hypertension increases with increasing concentrations of progestogens.

Women with a history of hypertension or hypertension-related diseases or renal disease (76) should be encouraged to use another method of contraception. If women elect to use oral contraceptives, they should be monitored closely, and if significant elevation of blood pressure occurs, oral contraceptives should be discontinued. For most women, elevated blood pressure will return to normal after stopping oral contraceptives (75), and there is no difference in the occurrence of hypertension among ever and never users. (74,76,77)

11. Headache

The onset or exacerbation of migraine or development of headache with a new pattern which is recurrent, persistent, or severe requires discontinuation of oral contraceptives and evaluation of the cause.

12. Bleeding Irregularities

Breakthrough bleeding and spotting are sometimes encountered in patients on oral contraceptives, especially during the first three months of use. Non-hormonal causes should be considered, and adequate diagnostic measures taken to rule out malignancy or pregnancy in the event of breakthrough bleeding, as in the case of any abnormal vaginal bleeding. If pathology has been excluded, time or a change to another formulation may solve the problem. In the event of amenorrhea, pregnancy should be ruled out.

Some women may encounter post-pill amenorrhea or oligomenorrhea, especially when such a condition was preexistent.

PRECAUTIONS

2. Physical Examination and Follow-Up

It is good medical practice for all women to have annual history and physical examinations, including women using oral contraceptives. The physical examination, however, may be deferred until after initiation of oral contraceptives if requested by the woman and judged appropriate by the clinician. The physical examination should include special reference to blood pressure, breasts, abdomen and pelvic organs, including cervical cytology, and relevant laboratory tests. In case of undiagnosed, persistent or recurrent abnormal vaginal bleeding, appropriate measures should be conducted to rule out malignancy. Women with a strong family history of breast cancer or who have breast nodules should be monitored with particular care.

3. Lipid Disorders

Women who are being treated for hyperlipidemia should be followed closely if they elect to use oral contraceptives. Some progestogens may elevate LDL levels and may render the control of hyperlipidemias more difficult.

4. Liver Function

If jaundice develops in any woman receiving such drugs, the medication should be discontinued. Steroid hormones may be poorly metabolized in patients with impaired liver function.

5. Fluid Retention

Oral contraceptives may cause some degree of fluid retention. They should be prescribed with caution, and only with careful monitoring, in patients with conditions which might be aggravated by fluid retention.

6. Emotional Disorders

Women with a history of depression should be carefully observed and the drug discontinued if depression recurs to a serious degree.

7. Contact Lenses

Contact lens wearers who develop visual changes or changes in lens tolerance should be assessed by an ophthalmologist.

8. Drug Interactions

Effects of Other Drugs on Oral Contraceptives (78)
Rifampin: Metabolism of both norethindrone and ethinyl estradiol is increased by rifampin. A reduction in contraceptive effectiveness and increased incidence of breakthrough bleeding and menstrual irregularities have been associated with concomitant use of rifampin.

Anticonvulsants: Anticonvulsants such as phenobarbital, phenytoin, and carbamazepine, have been shown to increase the metabolism of ethinyl estradiol and/or norethindrone, which could result in a reduction in contraceptive effectiveness.

Troglitazone: Administration of troglitazone with an oral contraceptive containing ethinyl estradiol and norethindrone reduced the plasma concentrations of both by approximately 30%, which could result in a reduction in contraceptive effectiveness.

Antibiotics: Pregnancy while taking oral contraceptives has been reported when the oral contraceptives were administered with antimicrobials such as ampicillin, tetracycline, and griseofulvin. However, clinical pharmacokinetic studies have not demonstrated any consistent effect of antibiotics (other than rifampin) on plasma concentrations of synthetic steroids.

Atorvastatin: Coadministration of atorvastatin and an oral contraceptive increased AUC values for norethindrone and ethinyl estradiol by approximately 30% and 20%, respectively.

Concomitant Use with HCV Combination Therapy= Liver Enzyme Elevation: Do not co-administer MICROGESTIN and MICROGESTIN Fe with HCV drug combinations containing ombitasvir/paritaprevir/ritonavir, with or without dasabuvir, due to the potential for ALT elevations (see Warnings, RISK OF LIVER ENZYME ELEVATIONS WITH CONCOMITANT HEPATITIS C TREATMENT)

Other: Ascorbic acid and acetaminophen may increase plasma ethinyl estradiol concentrations, possibly by inhibition of conjugation. A reduction in contraceptive effectiveness and increased incidence of breakthrough bleeding has been suggested with phenylbutazone.

Effects of Oral Contraceptives on Other Drugs

Oral contraceptive combinations containing ethinyl estradiol may inhibit the metabolism of other compounds. Increased plasma concentrations of cyclosporine, prednisolone, and theophylline have been reported with concomitant administration of oral contraceptives. In addition, oral contraceptives may induce the conjugation of other compounds. Decreased plasma concentrations of acetaminophen and increased clearance of temazepam, salicylic acid, morphine, and clofibric acid have been noted when these drugs were administered with oral contraceptives.

9. Interactions With Laboratory Tests

Certain endocrine and liver function tests and blood components may be affected by oral contraceptives:

a. Increased prothrombin and factors VII, VIII, IX, and X; decreased antithrombin 3; increased norepinephrine-induced platelet aggregability.

b. Increased thyroid binding globulin (TBG) leading to increased circulating total thyroid hormone, as measured by protein-bound iodine (PBI), T4 by column or by radioimmunoassay. Free T3 resin uptake is decreased, reflecting the elevated TBG; free T4 concentration is unaltered.

c. Other binding proteins may be elevated in serum.

d. Sex-binding globulins are increased and result in elevated levels of total circulating sex steroids and corticoids; however, free or biologically active levels remain unchanged.

e. Triglycerides may be increased.

f. Glucose tolerance may be decreased.

g. Serum folate levels may be depressed by oral contraceptive therapy. This may be of clinical significance if a woman becomes pregnant shortly after discontinuing oral contraceptives.

10. Carcinogenesis

See WARNINGS section.

11. Pregnancy

See CONTRAINDICATIONS and WARNINGS sections.

12. Nursing Mothers

Small amounts of oral contraceptive steroids have been identified in the milk of nursing mothers, and a few adverse effects on the child have been reported, including jaundice and breast enlargement. In addition, oral contraceptives given in the postpartum period may interfere with lactation by decreasing the quantity and quality of breast milk. If possible, the nursing mother should be advised not to use oral contraceptives but to use other forms of contraception until she has completely weaned her child.

13. Pediatric Use

Safety and efficacy of MICROGESTIN have been established in women of reproductive age. Safety and efficacy are expected to be the same for postpubertal adolescents under the age of 16 and for users 16 years and older. Use of this product before menarche is not indicated.

INFORMATION FOR THE PATIENT

See patient labeling printed below.

ADVERSE REACTIONS

An increased risk of the following serious adverse reactions has been associated with the use of oral contraceptives (see WARNINGS section):

- Thrombophlebitis
- Arterial thromboembolism
- Pulmonary embolism
- Myocardial infarction
- Cerebral hemorrhage
- Cerebral thrombosis
- Hypertension
- Gallbladder disease
- Hepatic adenomas or benign liver tumors

There is evidence of an association between the following conditions and the use of oral contraceptives, although additional confirmatory studies are needed:

- Mesenteric thrombosis
- Retinal thrombosis

The following adverse reactions have been reported in patients receiving oral contraceptives and are believed to be drug-related:

- Nausea
- Vomiting
- Gastrointestinal symptoms (such as abdominal cramps and bloating)
- Breakthrough bleeding
- Spotting
- Change in menstrual flow
- Amenorrhea
- Temporary infertility after discontinuation of treatment
- Edema
- Melasma which may persist
- Breast changes: tenderness, enlargement, secretion
- Change in weight (increase or decrease)
- Change in cervical erosion and secretion
- Diminution in lactation when given immediately postpartum
- Cholestatic jaundice
- Migraine
- Rash (allergic)
- Mental depression
- Reduced tolerance to carbohydrates
- Vaginal candidiasis
- Change in corneal curvature (steepening)
- Intolerance to contact lenses

The following adverse reactions have been reported in users of oral contraceptives and the association has been neither confirmed nor refuted:

- Pre-menstrual syndrome
- Cataracts
- Changes in appetite
- Cystitis-like syndrome
- Headache
- Nervousness
- Dizziness
- Hirsutism
- Loss of scalp hair
- Erythema multiforme
- Erythema nodosum
- Hemorrhagic eruption
- Vaginitis
- Porphyria
- Impaired renal function
- Hemolytic uremic syndrome
- Budd-Chiari syndrome
- Acne
- Changes in libido
- Colitis

OVERDOSAGE

Serious ill effects have not been reported following acute ingestion of large doses of oral contraceptives by young children. Overdosage may cause nausea, and withdrawal bleeding may occur in females.

NON-CONTRACEPTIVE HEALTH BENEFITS

The following non-contraceptive health benefits related to the use of oral contraceptives are supported by epidemiological studies which largely utilized oral contraceptive formulations containing estrogen doses exceeding 0.035 mg of ethinyl estradiol or 0.05 mg of mestranol. (79-84)

Effects on menses:

- Increased menstrual cycle regularity
- Decreased blood loss and decreased incidence of iron deficiency anemia
- Decreased incidence of dysmenorrhea

Effects related to inhibition of ovulation:

- Decreased incidence of functional ovarian cysts
- Decreased incidence of ectopic pregnancies

Effects from long-term use:

- Decreased incidence of fibroadenomas and fibrocystic disease of the breast
- Decreased incidence of acute pelvic inflammatory disease
- Decreased incidence of endometrial cancer
- Decreased incidence of ovarian cancer

DOSAGE AND ADMINISTRATION

The tablet dispenser has been designed to make oral contraceptive dosing as easy and as convenient as possible. The tablets are arranged in either three or four rows of seven tablets each, with the days of the week appearing on the tablet dispenser above the first row of tablets.

Note: Each tablet dispenser has been preprinted with the days of the week, starting with Sunday, to facilitate a Sunday-Start regimen. Six different day label strips have been provided with the Detailed Patient & Brief Summary Patient Package Insert in order to accommodate a Day-1 Start regimen. If the patient is using the Day-1 Start regimen, she should place the self-adhesive day label strip that corresponds to her starting day over the preprinted days.

Important: The patient should be instructed to use an additional method of protection until after the first week of administration in the initial cycle when utilizing the Sunday-Start regimen.

The possibility of ovulation and conception prior to initiation of use should be considered.

Dosage and Administration for 21-Day Dosage Regimen
To achieve maximum contraceptive effectiveness, MICROGESTIN must be taken exactly as directed and at intervals not exceeding 24 hours. MICROGESTIN provides the patient with a convenient tablet schedule of “3 weeks on—1 week off”. Two dosage regimens are described, one of which may be more convenient or suitable than the other for an individual patient. For the initial cycle of therapy, the patient begins her tablets according to the Day-1 Start or Sunday-Start regimen. With either regimen, the patient takes one tablet daily for 21 consecutive days followed by one week of no tablets.

A. Sunday-Start Regimen: The patient begins taking tablets from the top row on the first Sunday after menstrual flow begins. When menstrual flow begins on Sunday, the first tablet is taken on the same day. The last tablet in the dispenser will then be taken on a Saturday, followed by no tablets for a week (7 days). For all subsequent cycles, the patient then begins a new 21-tablet regimen on the eighth day, Sunday, after taking her last tablet. Following this regimen, of 21 days on—7 days off, the patient will start all subsequent cycles on a Sunday.

B. Day-1 Regimen: The first day of menstrual flow is Day 1. The patient places the self-adhesive day label strip that corresponds to her starting day over the preprinted days on the tablet dispenser. She starts taking one tablet daily, beginning with the first tablet in the top row. The patient completes her 21-tablet regimen when she has taken the last tablet in the tablet dispenser. She will then take no tablets for a week (7 days). For all subsequent cycles, the patient begins a new 21-tablet regimen on the eighth day after taking her last tablet, again starting with the first tablet in the top row after placing the appropriate day label strip over the preprinted days on the tablet dispenser. Following this regimen of 21 days on—7 days off, the patient will start all subsequent cycles on the same day of the week as the first course. Likewise, the interval of no tablets will always start on the same day of the week.

Tablets should be taken regularly with a meal or at bedtime. It should be stressed that efficacy of medication depends on strict adherence to the dosage schedule.

Special Notes on Administration
Menstruation usually begins two or three days, but may begin as late as the fourth or fifth day, after discontinuing medication. If spotting occurs while on the usual regimen of one tablet daily, the patient should continue medication without interruption.

If the patient forgets to take one or more tablets, the following is suggested:

One tablet is missed

- take tablet as soon as remembered
- take next tablet at the regular time

Two consecutive tablets are missed (week 1 or week 2)

- take two tablets as soon as remembered
- take two tablets the next day
- use another birth control method for seven days following the missed tablets

Two consecutive tablets are missed (week 3)
Sunday-Start Regimen:

- take one tablet daily until Sunday
- discard remaining tablets
- start new pack of tablets immediately (Sunday)
- use another birth control method for seven days following the missed tablets

Day-1 Start Regimen:

- discard remaining tablets
- start new pack of tablets that same day
- use another birth control method for seven days following the missed tablets

Three (or more) consecutive tablets are missed

Sunday-Start Regimen:

- take one tablet daily until Sunday
- discard remaining tablets
- start new pack of tablets immediately (Sunday)
- use another birth control method for seven days following the missed tablets

Day-1 Start Regimen:

- discard remaining tablets
- start new pack of tablets that same day
- use another birth control method for seven days following the missed tablets

The possibility of ovulation occurring increases with each successive day that scheduled tablets are missed. While there is little likelihood of ovulation occurring if only one tablet is missed, the possibility of spotting or bleeding is increased. This is particularly likely to occur if two or more consecutive tablets are missed.

In the rare case of bleeding which resembles menstruation, the patient should be advised to discontinue medication and then begin taking tablets from a new tablet dispenser on the next Sunday or the first day (Day 1), depending on her regimen. Persistent bleeding which is not controlled by this method indicates the need for reexamination of the patient, at which time nonfunctional causes should be considered.

Dosage and Administration for 28-Day Dosage Regimen
To achieve maximum contraceptive effectiveness, MICROGESTIN Fe should be taken exactly as directed and at intervals not exceeding 24 hours.

MICROGESTIN Fe provides a continuous administration regimen consisting of 21 light-colored (white or green) tablets of MICROGESTIN and 7 brown non-hormone containing tablets of ferrous fumarate. The ferrous fumarate tablets are present to facilitate ease of drug administration via a 28-day regimen and do not serve any therapeutic purpose. There is no need for the patient to count days between cycles because there are no "off-tablet days."

A. Sunday-Start Regimen: The patient begins taking the first light-colored tablet from the top row of the dispenser (labeled Sunday) on the first Sunday after menstrual flow begins. When the menstrual flow begins on Sunday, the first light-colored tablet is taken on the same day. The patient takes one light-colored tablet daily for 21 days. The last light-colored tablet in the dispenser will be taken on a Saturday. Upon completion of all 21 light-colored tablets, and without interruption, the patient takes one brown tablet daily for 7 days. Upon completion of this first course of tablets, the patient begins a second course of 28-day tablets, without interruption, the next day (Sunday), starting with the Sunday light-colored tablet in the top row. Adhering to this regimen of one light-colored tablet daily for 21 days, followed without interruption by one brown tablet daily for seven days, the patient will start all subsequent cycles on a Sunday.

B. Day-1 Start Regimen: The first day of menstrual flow is Day 1. The patient places the self-adhesive day label strip that corresponds to her starting day over the preprinted days on the tablet dispenser. She starts taking one light-colored tablet daily, beginning with the first light-colored tablet in the top row. After the last light-colored tablet (at the end of the third row) has been taken, the patient will then take the brown tablets for a week (7 days). For all subsequent cycles, the patient begins a new 28 tablet regimen on the eighth day after taking her last light-colored tablet, again starting with the first tablet in the top row after placing the appropriate day label strip over the preprinted days on the tablet dispenser. Following this regimen of 21 light-colored tablets and 7 brown tablets, the patient will start all subsequent cycles on the same day of the week as the first course.

Tablets should be taken regularly with a meal or at bedtime. It should be stressed that efficacy of medication depends on strict adherence to the dosage schedule.

Special Notes on Administration
Menstruation usually begins two or three days, but may begin as late as the fourth or fifth day, after the brown tablets have been started. In any event, the next course of tablets should be started without interruption. If spotting occurs while the patient is taking light-colored tablets, continue medication without interruption.

If the patient forgets to take one or more light-colored tablets, the following is suggested:

One tablet is missed

- take tablet as soon as remembered
- take next tablet at the regular time

Two consecutive tablets are missed (week 1 or week 2)

- take two tablets as soon as remembered
- take two tablets the next day
- use another birth control method for seven days following the missed tablets

Two consecutive tablets are missed (week 3)
Sunday-Start Regimen:

- take one tablet daily until Sunday
- discard remaining tablets
- start new pack of tablets immediately (Sunday)
- use another birth control method for seven days following the missed tablets

Day-1 Start Regimen:

- discard remaining tablets
- start new pack of tablets that same day
- use another birth control method for seven days following the missed tablets

Three (or more) consecutive tablets are missed

Sunday-Start Regimen:

- take one tablet daily until Sunday
- discard remaining tablets
- start new pack of tablets immediately (Sunday)
- use another birth control method for seven days following the missed tablets

Day-1 Start Regimen:

- discard remaining tablets
- start new pack of tablets that same day
- use another birth control method for seven days following the missed tablets

The possibility of ovulation occurring increases with each successive day that scheduled light-colored tablets are missed. While there is little likelihood of ovulation occurring if only one light-colored tablet is missed, the possibility of spotting or bleeding is increased. This is particularly likely to occur if two or more consecutive light-colored tablets are missed.

If the patient forgets to take any of the seven brown tablets in week four, those brown tablets that were missed are discarded and one brown tablet is taken each day until the pack is empty. A back-up birth control method is not required during this time. A new pack of tablets should be started no later than the eighth day after the last light-colored tablet was taken.

In the rare case of bleeding which resembles menstruation, the patient should be advised to discontinue medication and then begin taking tablets from a new tablet dispenser on the next Sunday or the first day (Day-1), depending on her regimen. Persistent bleeding which is not controlled by this method indicates the need for reexamination of the patient, at which time nonfunctional causes should be considered.

Use of Oral Contraceptives in the Event of a Missed Menstrual Period

1. If the patient has not adhered to the prescribed dosage regimen, the possibility of pregnancy should be considered after the first missed period and oral contraceptives should be withheld until pregnancy has been ruled out.

2. If the patient has adhered to the prescribed regimen and misses two consecutive periods, pregnancy should be ruled out before continuing the contraceptive regimen.

After several months on treatment, bleeding may be reduced to a point of virtual absence. This reduced flow may occur as a result of medication, in which event it is not indicative of pregnancy.

HOW SUPPLIED

Product: 53002-1549

NDC: 53002-1549-1 1 TABLET in a BLISTER PACK / 1 in a PACKAGE

NDC: 53002-1549-3 1 TABLET in a BLISTER PACK / 3 in a PACKAGE

NDC: 53002-1549-6 1 TABLET in a BLISTER PACK / 6 in a PACKAGE

REFERENCES

1. Back DJ, Breckenridge AM, Crawford FE, McIver M, Orme ML’E, Rowe PH and Smith E: Kinetics of norethindrone in women II. Single-dose kinetics. Clin Pharmacol Ther 1978; 24:448-453.
2. Hümpel M, Nieuweboer B, Wendt H and Speck U: Investigations of pharmacokinetics of ethinyloestradiol to specific consideration of a possible first-pass effect in women. Contraception 1979;19:421-432.
3. Back DJ, Breckenridge AM, Crawford FE, MacIver M, Orme ML’E, Rowe PH and Watts MJ. An investigation of the pharmacokinetics of ethynylestradiol in women using radioimmunoassay. Contraception 1979; 20:263-273.
4. Hammond GL, Lähteenmäki PLA, Lähteenmäki P and Luukkainen T. Distribution and percentages of non-protein bound contraceptive steroids in human serum. J Steriod Biochem 1982;17:375-380.
5. Fotherby K. Pharmacokinetics and metabolism of progestins in humans, in Pharmacology of the contraceptive steroids, Goldzieher JW, Fotherby K (eds), Raven Press, Ltd., New York, 1994; 99-126.
6. Goldzieher JW. Pharmacokinetics and metabolism of ethynyl estrogens, in Pharmacology of the contraceptive steroids, Goldzieher JW, Fotherby K (eds), Raven Press Ltd., New York, 1994; 127-151.
7. Hatcher RA, et al. 1998. Contraceptive Technology, Seventeenth Edition. New York: Irvington Publishers.
8. Stadel, B.V.: Oral contraceptives and cardiovascular disease. (Pt. 1). New England Journal of Medicine, 305:612-618, 1981.
9. Stadel, B.V.: Oral contraceptives and cardiovascular disease. (Pt. 2). New England Journal of Medicine, 305:672-677, 1981.
10. Adam, S.A., and M. Thorogood: Oral contraception and myocardial infarction revisited: The effects of new preparations and prescribing patterns. Brit. J. Obstet. and Gynec., 88:838-845, 1981.
11. Mann, J.I., and W.H. Inman: Oral contraceptives and death from myocardial infarction. Brit. Med. J., 2(5965): 245-248, 1975.
12. Mann, J.I., M.P. Vessey, M. Thorogood, and R. Doll: Myocardial infarction in young women with special reference to oral contraceptive practice. Brit. Med. J., 2(5956):241-245, 1975.
13. Royal College of General Practitioners’ Oral Contraception Study: Further analyses of mortality in oral contraceptive users. Lancet, 1:541-546, 1981.
14. Slone, D., S. Shapiro, D.W. Kaufman, L. Rosenberg, O.S. Miettinen, and P.D. Stolley: Risk of myocardial infarction in relation to current and discontinued use of oral contraceptives. N.E.J.M., 305:420-424, 1981.
15. Vessey, M.P.: Female hormones and vascular disease: An epidemiological overview. Brit. J. Fam.Plann., 6:1-12, 1980.
16. Russell-Briefel, R.G., T.M. Ezzati, R. Fulwood, J.A. Perlman, and R.S. Murphy: Cardiovascular risk status and oral contraceptive use, United States, 1976-80. Preventive Medicine, 15:352-362, 1986.
17. Goldbaum, G.M., J.S. Kendrick, G.C. Hogelin, and E.M. Gentry: The relative impact of smoking and oral contraceptive use on women in the United States. J.A.M.A., 258:1339-1342, 1987.
18. Layde, P.M., and V. Beral: Further analyses of mortality in oral contraceptive users: Royal College General Practitioners’ Oral Contraception Study. (Table 5) Lancet, 1:541-546, 1981.
19. Knopp, R.H.: Arteriosclerosis risk: The roles of oral contraceptives and postmenopausal estrogens. J. ofReprod. Med., 31(9)(Supplement): 913-921, 1986.
20. Krauss, R.M., S. Roy, D.R. Mishell, J. Casagrande, and M.C. Pike: Effects of two low-dose oral contraceptives on serum lipids and lipoproteins: Differential changes in high-density lipoproteins subclasses. Am. J. Obstet. Gyn., 145:446-452, 1983.
21. Wahl, P., C. Walden, R. Knopp, J. Hoover, R. Wallace, G. Heiss, and B. Rifkind: Effect of estrogen/progestin potency on lipid/lipoprotein cholesterol. N.E.J.M., 308:862-867, 1983.
22. Wynn, V., and R. Niththyananthan: The effect of progestin in combined oral contraceptives on serum lipids with special reference to high-density lipoproteins. Am. J. Obstet. and Gyn., 142:766-771, 1982.
23. Wynn, V., and I. Godsland: Effects of oral contraceptives on carbohydrate metabolism. J. Reprod.Medicine, 31 (9)(Supplement): 892-897, 1986.
24. LaRosa, J.C.: Atherosclerotic risk factors in cardiovascular disease. J. Reprod. Med., 31(9)(Supplement): 906-912, 1986.
25. Inman, W.H., and M.P. Vessey: Investigations of death from pulmonary, coronary, and cerebral thrombosis and embolism in women of child-bearing age. Brit. Med. J., 2(5599): 193-199, 1968.
26. Maguire, M.G., J. Tonascia, P.E. Sartwell, P.D. Stolley, and M.S. Tockman: Increased risk of thrombosis due to oral contraceptives: A further report. Am. J. Epidemiology, 110(2): 188-195, 1979.
27. Pettiti, D.B., J. Wingerd, F. Pellegrin, and S. Ramacharan: Risk of vascular disease in women: Smoking, oral contraceptives, noncontraceptive estrogens, and other factors. J.A.M.A., 242:1150-1154, 1979.
28. Vessey, M.P., and R. Doll: Investigation of relation between use of oral contraceptives and thromboembolic disease. Brit. Med. J., 2(5599): 199-205, 1968.
29. Vessey, M.P., and R. Doll: Investigation of relation between use of oral contraceptives and thromboembolic disease: A further report. Brit. Med. J., 2(5658): 651-657, 1969.
30. Porter, J.B., J.R. Hunter, D.A. Danielson, H. Jick, and A. Stergachis: Oral contraceptives and non-fatal vascular disease: Recent experience. Obstet. and Gyn., 59(3):299-302, 1982.
31. Vessey, M., R. Doll, R. Peto, B. Johnson, and P. Wiggins: A long-term follow-up study of women using different methods of contraception: An interim report. J. Biosocial. Sci., 8:375-427, 1976.
32. Royal College of General Practitioners: Oral contraceptives, venous thrombosis, and varicose veins. J.of Royal College of General Practitioners, 28:393-399, 1978.
33. Collaborative Group for the study of stroke in young women: Oral contraception and increased risk of cerebral ischemia or thrombosis. N.E.J.M., 288:871-878, 1973.
34. Petitti, D.B., and J. Wingerd: Use of oral contraceptives, cigarette smoking, and risk of subarachnoid hemorrhage. Lancet, 2:234-236, 1978.
35. Inman, W.H.: Oral contraceptives and fatal subarachnoid hemorrhage. Brit. Med. J., 2(6203): 1468-70, 1979.
36. Collaborative Group for the study of stroke in young women: Oral contraceptives and stroke in young women: Associated risk factors. J.A.M.A., 231:718-722, 1975.
37. Inman, W.H., M.P. Vessey, B. Westerholm, and A. Engelund: Thromboembolic disease and the steroidal content of oral contraceptives. A report to the Committee on Safety of Drugs. Brit. Med. J., 2:203-209, 1970.
38. Meade, T.W., G. Greenberg, and S.G. Thompson: Progestogens and cardiovascular reactions associated with oral contraceptives and a comparison of the safety of 50- and 35-mcg oestrogen preparations. Brit.Med. J., 280(6224): 1157-1161, 1980.
39. Kay, C.R.: Progestogens and arterial disease: Evidence from the Royal College of General Practitioners’ study. Amer. J. Obstet. Gyn., 142:762-765, 1982.
40. Royal College of General Practitioners: Incidence of arterial disease among oral contraceptive users. J.Coll. Gen. Pract., 33:75-82, 1983.
41. Ory, H.W: Mortality associated with fertility and fertility control:1983. Family Planning Perspectives, 15:50-56, 1983.
42. The Cancer and Steroid Hormone Study of the Centers for Disease Control and the National Institute of Child Health and Human Development: Oral-contraceptive use and the risk of breast cancer. N.E.J.M., 315: 405-411, 1986.
43. Pike, M.C., B.E. Henderson, M.D. Krailo, A. Duke, and S. Roy: Breast cancer in young women and use of oral contraceptives: Possible modifying effect of formulation and age at use. Lancet, 2:926-929, 1983.
44. Paul, C., D.G. Skegg, G.F.S. Spears, and J.M. Kaldor: Oral contraceptives and breast cancer: A national study. Brit. Med. J., 293:723-725, 1986.
45. Miller, D.R., L. Rosenberg, D.W. Kaufman, D. Schottenfeld, P.D. Stolley, and S. Shapiro: Breast cancer risk in relation to early oral contraceptive use. Obstet. Gynec., 68:863-868, 1986.
46. Olson, H., K.L. Olson, T.R. Moller, J. Ranstam, P. Holm: Oral contraceptive use and breast cancer in young women in Sweden (letter). Lancet, 2:748-749, 1985.
47. McPherson, K., M. Vessey, A. Neil, R. Doll, L. Jones, and M. Roberts: Early contraceptive use and breast cancer: Results of another case-control study. Brit. J. Cancer, 56: 653-660, 1987.
48. Huggins, G.R., and P.F. Zucker: Oral contraceptives and neoplasia: 1987 update. Fertil. Steril., 47:733-761, 1987.
49. McPherson, K., and J.O. Drife: The pill and breast cancer: Why the uncertainty? Brit. Med. J., 293:709-710, 1986.
50. Shapiro, S.: Oral contraceptives: Time to take stock. N.E.J.M., 315:450-451, 1987.
51. Ory, H., Z. Naib, S.B. Conger, R.A. Hatcher, and C.W. Tyler: Contraceptive choice and prevalence of cervical dysplasia and carcinoma in situ. Am. J. Obstet. Gynec., 124:573-577, 1976.
52. Vessey, M.P., M. Lawless, K. McPherson, D. Yeates: Neoplasia of the cervix uteri and contraception: A possible adverse effect of the pill. Lancet, 2:930, 1983.
53. Brinton, L.A., G.R. Huggins, H.F. Lehman, K. Malli, D.A. Savitz, E. Trapido, J. Rosenthal, and R. Hoover: Long-term use of oral contraceptives and risk of invasive cervical cancer. Int. J. Cancer, 38:339-344, 1986.
54. WHO Collaborative Study of Neoplasia and Steroid Contraceptives: Invasive cervical cancer and combined oral contraceptives. Brit. Med. J., 290:961-965, 1985.
55. Rooks, J.B., H.W. Ory, K.G. Ishak, L.T. Strauss, J.R. Greenspan, A.P. Hill, and C.W. Tyler: Epidemiology of hepatocellular adenoma: The role of oral contraceptive use. J.A.M.A., 242:644-648, 1979.
56. Bein, N.N., and H.S. Goldsmith: Recurrent massive hemorrhage from benign hepatic tumors secondary to oral contraceptives. Brit. J. Surg., 64:433-435, 1977.
57. Klatskin, G.: Hepatic tumors: Possible relationship to use of oral contraceptives. Gastroenterology, 73:386-394, 1977.
58. Henderson, B.E., S. Preston-Martin, H.A. Edmondson, R.L. Peters, and M.C. Pike: Hepatocellular carcinoma and oral contraceptives. Brit. J. Cancer, 48:437-440, 1983.
59. Neuberger, J., D. Forman, R. Doll, and R. Williams: Oral contraceptives and hepatocellular carcinoma. Brit. Med. J., 292:1355-1357, 1986.
60. Forman, D., T.J. Vincent, and R. Doll: Cancer of the liver and oral contraceptives. Brit. Med. J., 292: 1357-1361, 1986.
61. Harlap, S., and J. Eldor: Births following oral contraceptive failures. Obstet. Gynec., 55:447-452, 1980.
62. Savolainen, E., E. Saksela, and L. Saxen: Teratogenic hazards of oral contraceptives analyzed in a national malformation register. Amer. J. Obstet. Gynec., 140:521-524, 1981.
63. Janerich, D.T., J.M. Piper, and D.M. Glebatis: Oral contraceptives and birth defects. Am. J.Epidemiology, 112:73-79, 1980.
64. Ferencz, C., G.M. Matanoski, P.D. Wilson, J.D. Rubin, C.A. Neill, and R. Gutberlet: Maternal hormone therapy and congenital heart disease. Teratology, 21:225-239, 1980.
65. Rothman, K.J., D.C. Fyler, A. Goldbatt, and M.B. Kreidberg: Exogenous hormones and other drug exposures of children with congenital heart disease. Am. J. Epidemiology, 109:433-439, 1979.
66. Boston Collaborative Drug Surveillance Program: Oral contraceptives and venous thromboembolic disease, surgically confirmed gallbladder disease, and breast tumors. Lancet, 1:1399-1404, 1973.
67. Royal College of General Practitioners: Oral Contraceptives and Health. New York, Pittman, 1974, 100p.
68. Layde, P.M., M.P. Vessey, and D. Yeates: Risk of gallbladder disease: A cohort study of young women attending family planning clinics. J. of Epidemiol. and Comm. Health, 36: 274-278, 1982.
69. Rome Group for the Epidemiology and Prevention of Cholelithiasis (GREPCO): Prevalence of gallstone disease in an Italian adult female population. Am. J. Epidemiol., 119:796-805, 1984.
70. Strom, B.L., R.T. Tamragouri, M.L. Morse, E.L. Lazar, S.L. West, P. D. Stolley, and J.K. Jones: Oral contraceptives and other risk factors for gallbladder disease. Clin. Pharmacol. Ther., 39:335-341, 1986.
71. Wynn, V., P.W. Adams, I.F. Godsland, J. Melrose, R. Niththyananthan, N.W. Oakley, and A. Seedj: Comparison of effects of different combined oral-contraceptive formulations on carbohydrate and lipid metabolism. Lancet, 1:1045-1049, 1979.
72. Wynn, V.: Effect of progesterone and progestins on carbohydrate metabolism. In Progesterone and Progestin. Edited by C.W. Bardin, E. Milgrom, P. Mauvis-Jarvis. New York, Raven Press, pp. 395-410, 1983.
73. Perlman, J.A., R. G. Roussell-Briefel, T.M. Ezzati, and G. Lieberknecht: Oral glucose tolerance and the potency of oral contraceptive progestogens. J. Chronic Dis., 38:857-864, 1985.
74. Royal College of General Practitioners’ Oral Contraception Study: Effect on hypertension and benign breast disease of progestogen component in combined oral contraceptives. Lancet, 1:624, 1977.
75. Fisch, I.R., and J. Frank: Oral contraceptives and blood pressure. J.A.M.A., 237:2499-2503, 1977.
76. Laragh, A.J.: Oral contraceptive induced hypertension: Nine years later. Amer. J. Obstet. Gynecol., 126:141-147, 1976.
77. Ramcharan, S., E. Peritz, F.A. Pellegrin, and W.T. Williams: Incidence of hypertension in the Walnut Creek Contraceptive Drug Study cohort. In Pharmacology of Steroid Contraceptive Drugs. Edited by S. Garattini and H.W. Berendes. New York, Raven Press, pp. 277-288, 1977. (Monographs of the Mario Negri Institute for Pharmacological Research, Milan.)
78. Back DJ, Orme ML’E. Drug interactions, in Pharmacology of the contraceptive steroids. Goldzieher JW, Fotherby K (eds), Raven Press, Ltd., New York, 1994, 407-425.
79. The Cancer and Steroid Hormone Study of the Centers for Disease Control and the National Institute of Child Health and Human Development: Oral contraceptive use and the risk of ovarian cancer. J.A.M.A., 249:1596-1599, 1983.
80. The Cancer and Steroid Hormone Study of the Centers for Disease Control and the National Institute of Child Health and Human Development: Combination oral contraceptive use and the risk of endometrial cancer. J.A.M.A., 257:796-800, 1987.
81. Ory, H.W.: Functional ovarian cysts and oral contraceptives: Negative association confirmed surgically. J.A.M.A., 228:68-69, 1974.
82. Ory, H.W., P. Cole, B. Macmahon, and R. Hoover: Oral contraceptives and reduced risk of benign breast disease. N.E.J.M., 294:41-422, 1976.
83. Ory, H.W.: The noncontraceptive health benefits from oral contraceptive use. Fam. Plann. Perspectives, 14:182-184, 1982.
84. Ory, H.W., J.D. Forrest, and R. Lincoln: Making Choices: Evaluating the health risks and benefits of birth control methods. New York, The Alan Guttmacher Institute, p.1, 1983.
85. Miller, D.R., L. Rosenberg, D.W. Kaufman, P. Stolley, M.E. Warshauer, and S. Shapiro: Breast cancer before age 45 and oral contraceptive use: new findings. Am. J. Epidemiol., 129:269-280, 1989.
86. Kay, C.R., and P.C. Hannaford: Breast cancer and the pill: a further report from the Royal College of General Practitioners Oral Contraception Study. Br. J. Cancer, 58:675-680, 1988.
87. Stadel, B.V., S. Lai, J.J. Schlesselman, and P. Murray: Oral contraceptives and premenopausal breast cancer in nulliparous women. Contraception, 38:287-299, 1988.
88. UK National Case—Control Study Group: Oral contraceptive use and breast cancer risk in young women. Lancet, 973-982, 1989.
89. Romieu, I., W.C. Willett, G.A. Colditz, M.J. Stampfer, B. Rosner, C.H. Hennekens, and F.E. Speizer: Prospective study of oral contraceptive use and risk of breast cancer in women. J. Natl. Cancer Inst., 81:1313-1321, 1989.

Distributed by:
Mayne Pharma
Greenville, NC 27834

MICROGESTIN® is a registered trademark of Mayne Pharma LLC.

Revised: June 2020

MIC-001

The patient labeling for oral contraceptive drug products is set forth below:

BRIEF SUMMARY PATIENT PACKAGE INSERT

MICROGESTIN®
(Norethindrone Acetate and Ethinyl Estradiol Tablets, USP)

MICROGESTIN® 1/20
(Each white tablet contains 1 mg norethindrone acetate and 20 mcg ethinyl estradiol.)
MICROGESTIN® 1.5/30
(Each green tablet contains 1.5 mg norethindrone acetate and 30 mcg ethinyl estradiol.)

MICROGESTIN® Fe
(Norethindrone Acetate and Ethinyl Estradiol Tablets, USP and Ferrous Fumarate Tablets*)
*Ferrous fumarate tablets are not USP for dissolution and assay.

MICROGESTIN® Fe 1/20
(Each white tablet contains 1 mg norethindrone acetate and 20 mcg ethinyl estradiol. Each brown tablet contains 75 mg ferrous fumarate.)

MICROGESTIN® Fe 1.5/30
(Each green tablet contains 1.5 mg norethindrone acetate and 30 mcg ethinyl estradiol. Each brown tablet contains 75 mg ferrous fumarate.)

This product (like all oral contraceptives) is intended to prevent pregnancy. It does not protect against HIV infection (AIDS) and other sexually transmitted diseases.

Oral contraceptives, also known as “birth control pills” or “the pill,” are taken to prevent pregnancy and, when taken correctly, have a failure rate of about 1% per year when used without missing any pills. The typical failure rate of large numbers of pill users is less than 3% per year when women who miss pills are included. For most women oral contraceptives are also free of serious or unpleasant side effects. However, forgetting to take pills considerably increases the chances of pregnancy.

For the majority of women, oral contraceptives can be taken safely. But there are some women who are at high risk of developing certain serious diseases that can be life-threatening or may cause temporary or permanent disability. The risks associated with taking oral contraceptives increase significantly if you:

1. Smoke

2. Have high blood pressure, diabetes, high cholesterol

3. Have or have had clotting disorders, heart attack, stroke, angina pectoris, cancer of the breast or sex organs, jaundice, or malignant or benign liver tumors.

You should not take the pill if you suspect you are pregnant or have unexplained vaginal bleeding.

Cigarette smoking increases the risk of serious cardiovascular side effects from oral contraceptive use. This risk increases with age and with heavy smoking (15 or more cigarettes per day) and is quite marked in women over 35 years of age. Women who use oral contraceptives are strongly advised not to smoke.

Most side effects of the pill are not serious. The most common side effects are nausea, vomiting, bleeding between menstrual periods, weight gain, breast tenderness, and difficulty wearing contact lenses. These side effects, especially nausea, vomiting, and breakthrough bleeding may subside within the first three months of use.

The serious side effects of the pill occur very infrequently, especially if you are in good health and are young. However, you should know that the following medical conditions have been associated with or made worse by the pill:

1. Blood clots in the legs (thrombophlebitis), lungs (pulmonary embolism), stoppage or rupture of a blood vessel in the brain (stroke), blockage of blood vessels in the heart (heart attack or angina pectoris) or other organs of the body. As mentioned above, smoking increases the risk of heart attacks and strokes and subsequent serious medical consequences.

2. Liver tumors, which may rupture and cause severe bleeding. A possible but not definite association has been found with the pill and liver cancer. However, liver cancers are extremely rare. The chance of developing liver cancer from using the pill is thus even rarer.

3. High blood pressure, although blood pressure usually returns to normal when the pill is stopped.

The symptoms associated with these serious side effects are discussed in the detailed leaflet given to you with your supply of pills. Notify your doctor or healthcare provider if you notice any unusual physical disturbances while taking the pill. In addition, drugs such as rifampin, as well as some anticonvulsants and some antibiotics, may decrease oral contraceptive effectiveness.

Most of the studies to date on breast cancer and pill use have found no increase in the risk of developing breast cancer, although some studies have reported an increased risk of developing breast cancer in certain groups of women. However, some studies have found an increase in the risk of developing cancer of the cervix in women taking the pill, but this finding may be related to differences in sexual behavior or other factors not related to use of the pill. Therefore, there is insufficient evidence to rule out the possibility that the pill may cause cancer of the breast or cervix.

Taking the pill provides some important non-contraceptive benefits. These include less painful menstruation, less menstrual blood loss and anemia, fewer pelvic infections, and fewer cancers of the ovary and the lining of the uterus.

Be sure to discuss any medical condition you may have with your healthcare provider. Your healthcare provider will take a medical and family history and examine you before prescribing oral contraceptives. The physical examination may be delayed to another time if you request it and your healthcare provider believes that it is a good medical practice to postpone it. You should be reexamined at least once a year while taking oral contraceptives. The detailed patient information leaflet gives you further information which you should read and discuss with your healthcare provider.

This product (like all oral contraceptives) is intended to prevent pregnancy. It does not protect against transmission of HIV (AIDS) and other sexually transmitted diseases such as Chlamydia, genital herpes, genital warts, gonorrhea, hepatitis B and syphilis.

INSTRUCTIONS TO PATIENT

TABLET DISPENSER

The MICROGESTIN tablet dispenser has been designed to make oral contraceptive dosing as easy and as convenient as possible. The tablets are arranged in either three or four rows of seven tablets each with the days of the week appearing above the first row of tablets.

If your TABLET DISPENSER contains: | You are taking:
21 white tablets | MICROGESTIN 1/20
21 green tablets | MICROGESTIN 1.5/30
21 white tablets and 7 brown tablets | MICROGESTIN Fe 1/20
21 green tablets and 7 brown tablets | MICROGESTIN Fe 1.5/30

Each white tablet contains 1 mg norethindrone acetate and 20 mcg ethinyl estradiol.
Each green tablet contains 1.5 mg norethindrone acetate and 30 mcg ethinyl estradiol.
Each brown tablet contains 75 mg ferrous fumarate, and is intended to help you remember to take the tablets correctly. These brown tablets are not intended to have any health benefit.

DIRECTIONS

To remove a tablet, press down on it with your thumb or finger. The tablet will drop through the back of the tablet dispenser. Do not press with your thumbnail, fingernail, or any other sharp object.

HOW TO TAKE THE PILL

IMPORTANT POINTS TO REMEMBER

BEFORE YOU START TAKING YOUR PILLS:

1. BE SURE TO READ THESE DIRECTIONS:
Before you start taking your pills.
Anytime you are not sure what to do.

2. THE RIGHT WAY TO TAKE THE PILL IS TO TAKE ONE PILL EVERY DAY AT THE SAME TIME. If you miss pills you could get pregnant. This includes starting the pack late. The more pills you miss, the more likely you are to get pregnant.

3. MANY WOMEN HAVE SPOTTING OR LIGHT BLEEDING, OR MAY FEEL SICK TO THEIR STOMACH DURING THE FIRST 1-3 PACKS OF PILLS. If you do have spotting or light bleeding or feel sick to your stomach, do not stop taking the pill. The problem will usually go away. If it doesn’t go away, check with your doctor or clinic.

4. MISSING PILLS CAN ALSO CAUSE SPOTTING OR LIGHT BLEEDING, even when you make up these missed pills. On the days you take 2 pills to make up for missed pills, you could also feel a little sick to your stomach.

5. IF YOU HAVE VOMITING OR DIARRHEA, for any reason, or IF YOU TAKE SOME MEDICINES, including some antibiotics, your birth control pills may not work as well. Use a back-up birth control method (such as condoms or foam) until you check with your doctor or clinic.

6. IF YOU HAVE TROUBLE REMEMBERING TO TAKE THE PILL, talk to your doctor or clinic about how to make pill-taking easier or about using another method of birth control.

7. IF YOU HAVE ANY QUESTIONS OR ARE UNSURE ABOUT THE INFORMATION IN THIS LEAFLET, call your doctor or clinic.

BEFORE YOU START TAKING YOUR PILLS

1. DECIDE WHAT TIME OF DAY YOU WANT TO TAKE YOUR PILL. It is important to take it at about the same time every day.

2. LOOK AT YOUR PILL PACK TO SEE IF IT HAS 21 OR 28 PILLS:
The 21-Day pill pack has 21 "active" white or green pills (with hormones) to take for 3 weeks, followed by 1 week without pills.
The 28-Day pill pack has 21 "active" white or green pills (with hormones) to take for 3 weeks, followed by 1 week of reminder brown pills (without hormones).

3. ALSO FIND:
1) where on the pack to start taking pills,
2) in what order to take the pills (follow the arrows), and
3) the week numbers as shown in the following pictures:

MICROGESTIN 1/20 will contain: ALL WHITE PILLS.

MICROGESTIN 1.5/30 will contain: ALL GREEN PILLS.

MICROGESTIN Fe 1/20 will contain: 21 WHITE PILLS for WEEKS 1, 2, and 3.
WEEK 4 will contain BROWN PILLS ONLY.

MICROGESTIN Fe 1.5/30 will contain: 21 GREEN PILLS for WEEKS 1, 2, and 3.
WEEK 4 will contain BROWN PILLS ONLY.

4. BE SURE YOU HAVE READY AT ALL TIMES:
ANOTHER KIND OF BIRTH CONTROL (such as condoms or foam) to use as a back-up in case you miss pills.
An EXTRA, FULL PILL PACK.

WHEN TO START THE FIRST PACK OF PILLS

You have a choice of which day to start taking your first pack of pills. Decide with your doctor or clinic which is the best day for you. Pick a time of day which will be easy to remember.

DAY-1 START:

1. Pick the day label strip that starts with the first day of your period. (This is the day you start bleeding or spotting, even if it is almost midnight when the bleeding begins.)

2. Place this day label strip on the tablet dispenser over the area that has the days of the week (starting with Sunday) printed on the plastic.

3. Take the first "active" white or green pill of the first pack during the first 24 hours of your period.

4. You will not need to use a back-up method of birth control, since you are starting the pill at the beginning of your period.

SUNDAY START:

1. Take the first "active" white or green pill of the first pack on the Sunday after your period starts, even if you are still bleeding. If your period begins on Sunday, start the pack that same day.

2. Use another method of birth control as a back-up method if you have sex anytime from the Sunday you start your first pack until the next Sunday (7 days). Condoms or foam are good back-up methods of birth control.

WHAT TO DO DURING THE MONTH

1. TAKE ONE PILL AT THE SAME TIME EVERY DAY UNTIL THE PACK IS EMPTY.
Do not skip pills even if you are spotting or bleeding between monthly periods or feel sick to your stomach (nausea).
Do not skip pills even if you do not have sex very often.

2. WHEN YOU FINISH A PACK OR SWITCH YOUR BRAND OF PILLS:
21 pills: Wait 7 days to start the next pack. You will probably have your period during that week. Be sure that no more than 7 days pass between 21-day packs.
28 pills: Start the next pack on the day after your last "reminder" pill. Do not wait any days between packs.

WHAT TO DO IF YOU MISS PILLS

If you MISS 1 white or green "active" pill:

1. Take it as soon as you remember. Take the next pill at your regular time. This means you may take 2 pills in 1 day.

2. You do not need to use a back-up birth control method if you have sex.

If you MISS 2 white or green "active" pills in a row in WEEK 1 OR WEEK 2 of your pack:

1. Take 2 pills on the day you remember and 2 pills the next day.

2. Then take 1 pill a day until you finish the pack.

3. You COULD GET PREGNANT if you have sex in the 7 days after you miss pills. You MUST use another birth control method (such as condoms or foam) as a back-up method of birth control until you have taken a white or green "active" pill every day for 7 days.

If you MISS 2 white or green "active" pills in a row in THE 3rd WEEK:

1. If you are a Day-1 Starter:
THROW OUT the rest of the pill pack and start a new pack that same day.
If you are a Sunday Starter:
Keep taking 1 pill every day until Sunday. On Sunday, THROW OUT the rest of the pack and start a new pack of pills that same day.

2. You may not have your period this month, but this is expected. However, if you miss your period 2 months in a row, call your doctor or clinic because you might be pregnant.

3. You COULD GET PREGNANT if you have sex in the 7 days after you miss pills. You MUST use another birth control method (such as condoms or foam) as a back-up method of birth control until you have taken a white or green "active" pill every day for 7 days.

If you MISS 3 OR MORE white or green "active" pills in a row (during the first 3 weeks):

1. If you are a Day-1 Starter:
THROW OUT the rest of the pill pack and start a new pack that same day.
If you are a Sunday Starter:
Keep taking 1 pill every day until Sunday. On Sunday, THROW OUT the rest of the pack and start a new pack of pills that same day.

2. You may not have your period this month, but this is expected. However, if you miss your period 2 months in a row, call your doctor or clinic because you might be pregnant.

3. You COULD GET PREGNANT if you have sex in the 7 days after you miss pills. You MUST use another birth control method (such as condoms or foam) as a back-up method of birth control until you have taken a white or green "active" pill every day for 7 days.

A REMINDER FOR THOSE ON 28-DAY PACKS:
IF YOU FORGET ANY OF THE 7 BROWN "REMINDER" PILLS IN WEEK 4:
THROW AWAY THE PILLS YOU MISSED.
KEEP TAKING 1 PILL EACH DAY UNTIL THE PACK IS EMPTY.
YOU DO NOT NEED A BACK-UP METHOD.
FINALLY, IF YOU ARE STILL NOT SURE WHAT TO DO ABOUT THE PILLS YOU HAVE MISSED:
Use a BACK-UP METHOD anytime you have sex.
KEEP TAKING ONE WHITE OR GREEN "ACTIVE" PILL EACH DAY until you can reach your doctor or clinic.

Based on his or her assessment of your medical needs, your doctor or healthcare provider has prescribed this drug for you. Do not give this drug to anyone else.

Keep this and all drugs out of the reach of children.

Rx only

Store below 30º C (86º F).

Cigarette smoking increases the risk of serious cardiovascular side effects from oral contraceptive use. This risk increases with age and with heavy smoking (15 or more cigarettes per day) and is quite marked in women over 35 years of age. Women who use oral contraceptives are strongly advised not to smoke.

Distributed by:
Mayne Pharma
Greenville, NC 27834

MICROGESTIN® is a registered trademark of Mayne Pharma LLC.

Revised: June 2020

MICBPL-001

DETAILED PATIENT PACKAGE INSERT

MICROGESTIN®
(Norethindrone Acetate and Ethinyl Estradiol Tablets, USP)

MICROGESTIN® 1/20
(Each white tablet contains 1 mg norethindrone acetate and 20 mcg ethinyl estradiol.)
MICROGESTIN® 1.5/30
(Each green tablet contains 1.5 mg norethindrone acetate and 30 mcg ethinyl estradiol.)

MICROGESTIN® Fe
(Norethindrone Acetate and Ethinyl Estradiol Tablets, USP and Ferrous Fumarate Tablets*)
*Ferrous fumarate tablets are not USP for dissolution and assay.

MICROGESTIN® Fe 1/20
(Each white tablet contains 1 mg norethindrone acetate and 20 mcg ethinyl estradiol. Each brown tablet contains 75 mg ferrous fumarate.)

MICROGESTIN® Fe 1.5/30
(Each green tablet contains 1.5 mg norethindrone acetate and 30 mcg ethinyl estradiol. Each brown tablet contains 75 mg ferrous fumarate.)

This product (like all oral contraceptives) is intended to prevent pregnancy. It does not protect against HIV infection (AIDS) and other sexually transmitted diseases.

What You Should Know About Oral Contraceptives

Any woman who considers using oral contraceptives (the “birth control pill” or “the pill”) should understand the benefits and risks of using this form of birth control. This leaflet will give you much of the information you will need to make this decision and will also help you determine if you are at risk of developing any of the serious side effects of the pill. It will tell you how to use the pill properly so that it will be as effective as possible. However, this leaflet is not a replacement for a careful discussion between you and your healthcare provider. You should discuss the information provided in this leaflet with him or her, both when you first start taking the pill and during your revisits. You should also follow your healthcare provider’s advice with regard to regular check-ups while you are on the pill.

EFFECTIVENESS OF ORAL CONTRACEPTIVES

Oral contraceptives or “birth control pills” or “the pill” are used to prevent pregnancy and are more effective than other non-surgical methods of birth control. When they are taken correctly, the chance of becoming pregnant is less than 1% (1 pregnancy per 100 women per year of use) when used perfectly, without missing any pills. Typical failure rates are actually 3% per year. The chance of becoming pregnant increases with each missed pill during a menstrual cycle.

In comparison, typical failure rates for other methods of birth control during the first year of use are as follows:

Implant: < 1% | Male sterilization: < 1%
Injection: < 1% | Cervical Cap: 20 to 40%
IUD: < 1 to 2% | Condom alone (male): 14%
Diaphragm with spermicides: 20% | Condom alone (female): 21%
Spermicides alone: 26% | Periodic abstinence: 25%
Vaginal Sponge: 20 to 40% | Withdrawal: 19%
Female sterilization: < 1% | No method: 85%

WHO SHOULD NOT TAKE ORAL CONTRACEPTIVES

Cigarette smoking increases the risk of serious cardiovascular side effects from oral contraceptive use. This risk increases with age and with heavy smoking (15 or more cigarettes per day) and is quite marked in women over 35 years of age. Women who use oral contraceptives are strongly advised not to smoke.

Some women should not use the pill. For example, you should not take the pill if you are pregnant or think you may be pregnant. You should also not use the pill if you have any of the following conditions:

- A history of heart attack or stroke
- Blood clots in the legs (thrombophlebitis), lungs (pulmonary embolism), or eyes
- A history of blood clots in the deep veins of your legs
- Chest pain (angina pectoris)
- Known or suspected breast cancer or cancer of the lining of the uterus, cervix or vagina
- Unexplained vaginal bleeding (until a diagnosis is reached by your doctor)
- Yellowing of the whites of the eyes or of the skin (jaundice) during pregnancy or during previous use of the pill
- Liver tumor (benign or cancerous)
- Take any Hepatitis C drug combination ombitasvir/paritaprevir/ritonavir, with or without dasabuvir. This may increase levels of the liver enzyme “alanine aminotransferase” (ALT) in the blood
- Known or suspected pregnancy

Tell your healthcare provider if you have ever had any of these conditions. Your healthcare provider can recommend a safer method of birth control.

OTHER CONSIDERATIONS BEFORE TAKING ORAL CONTRACEPTIVES

Tell your healthcare provider if you have:

- Breast nodules, fibrocystic disease of the breast, an abnormal breast x-ray or mammogram
- Diabetes
- Elevated cholesterol or triglycerides
- High blood pressure
- Migraine or other headaches or epilepsy
- Mental depression
- Gallbladder, heart, or kidney disease
- History of scanty or irregular menstrual periods

Women with any of these conditions should be checked often by their healthcare provider if they choose to use oral contraceptives. Also, be sure to inform your doctor or healthcare provider if you smoke or are on any medications.

RISKS OF TAKING ORAL CONTRACEPTIVES

1. Risk of Developing Blood Clots

Blood clots and blockage of blood vessels are the most serious side effects of taking oral contraceptives; in particular, a clot in the legs can cause thrombophlebitis, and a clot that travels to the lungs can cause a sudden blocking of the vessel carrying blood to the lungs. Rarely, clots occur in the blood vessels of the eye and may cause blindness, double vision, or impaired vision.

If you take oral contraceptives and need elective surgery, need to stay in bed for a prolonged illness, or have recently delivered a baby, you may be at risk of developing blood clots. You should consult your doctor about stopping oral contraceptives three to four weeks before surgery and not taking oral contraceptives for two weeks after surgery or during bed rest. You should also not take oral contraceptives soon after delivery of a baby. It is advisable to wait for at least four weeks after delivery if you are not breastfeeding. If you are breastfeeding, you should wait until you have weaned your child before using the pill. (See also the section on Breastfeeding in GENERAL PRECAUTIONS.)

2. Heart Attacks and Strokes

Oral contraceptives may increase the tendency to develop strokes (stoppage or rupture of blood vessels in the brain) and angina pectoris and heart attacks (blockage of blood vessels in the heart). Any of these conditions can cause death or disability.

Smoking greatly increases the possibility of suffering heart attacks and strokes. Furthermore, smoking and the use of oral contraceptives greatly increase the chances of developing and dying of heart disease.

3. Gallbladder Disease

Oral contraceptive users probably have a greater risk than nonusers of having gallbladder disease, although this risk may be related to pills containing high doses of estrogens.

4. Liver Tumors

In rare cases, oral contraceptives can cause benign but dangerous liver tumors. These benign liver tumors can rupture and cause fatal internal bleeding. In addition, a possible but not definite association has been found with the pill and liver cancers in two studies, in which a few women who developed these very rare cancers were found to have used oral contraceptives for long periods. However, liver cancers are extremely rare. The chance of developing liver cancer from using the pill is thus even rarer.

5. Cancer of the Reproductive Organs and Breasts

There is, at present, no confirmed evidence that oral contraceptive use increases the risk of developing cancer of the reproductive organs. Studies to date of women taking the pill have reported conflicting findings on whether pill use increases the risk of developing cancer of the breast or cervix. Most of the studies on breast cancer and pill use have found no overall increase in the risk of developing breast cancer, although some studies have reported an increased risk of developing breast cancer in certain groups of women. Women who use oral contraceptives and have a strong family history of breast cancer or who have breast nodules or abnormal mammograms should be closely followed by their doctors.

Some studies have found an increase in the incidence of cancer of the cervix in women who use oral contraceptives. However, this finding may be related to factors other than the use of oral contraceptives.

ESTIMATED RISK OF DEATH FROM A BIRTH CONTROL METHOD OR PREGNANCY

All methods of birth control and pregnancy are associated with a risk of developing certain diseases which may lead to disability or death. An estimate of the number of deaths associated with different methods of birth control and pregnancy has been calculated and is shown in the following table.

ANNUAL NUMBER OF BIRTH-RELATED OR METHOD-RELATED DEATHS ASSOCIATED WITH CONTROL OF FERTILITY PER 100,000 NONSTERILE WOMEN BY FERTILITY CONTROL METHOD ACCORDING TO AGE

Method of control and outcome | 15-19 | 20-24 | 25-29 | 30-34 | 35-39 | 40-44
No fertility control methods* | 7.0 | 7.4 | 9.1 | 14.8 | 25.7 | 28.2
Oral contraceptives non-smoker** | 0.3 | 0.5 | 0.9 | 1.9 | 13.8 | 31.6
Oral contraceptives smoker** | 2.2 | 3.4 | 6.6 | 13.5 | 51.1 | 117.2
IUD** | 0.8 | 0.8 | 1.0 | 1.0 | 1.4 | 1.4
Condom* | 1.1 | 1.6 | 0.7 | 0.2 | 0.3 | 0.4
Diaphragm/spermicide* | 1.9 | 1.2 | 1.2 | 1.3 | 2.2 | 2.8
Periodic abstinence* | 2.5 | 1.6 | 1.6 | 1.7 | 2.9 | 3.6
*Deaths are birth related.
**Deaths are method related.

In the above table, the risk of death from any birth control method is less than the risk of childbirth, except for oral contraceptive users over the age of 35 who smoke and pill users over the age of 40 even if they do not smoke. It can be seen in the table that for women aged 15 to 39, the risk of death was highest with pregnancy (7-26 deaths per 100,000 women, depending on age). Among pill users who do not smoke, the risk of death was always lower than that associated with pregnancy for any age group, although over the age of 40, the risk increases to 32 deaths per 100,000 women, compared to 28 associated with pregnancy at that age. However, for pill users who smoke and are over the age of 35, the estimated number of deaths exceeds those for other methods of birth control. If a woman is over the age of 40 and smokes, her estimated risk of death is four times higher (117/100,000 women) than the estimated risk associated with pregnancy (28/100,000 women) in that age group.

The suggestion that women over 40 who don’t smoke should not take oral contraceptives is based on information from older higher dose pills and on less selective use of pills than is practiced today. An Advisory Committee of the FDA discussed this issue in 1989 and recommended that the benefits of oral contraceptive use by healthy, non-smoking women over 40 years of age may outweigh the possible risks. However, all women, especially older women, are cautioned to use the lowest dose pill that is effective.

WARNING SIGNALS

If any of these adverse effects occur while you are taking oral contraceptives, call your doctor immediately:

- Sharp chest pain, coughing of blood, or sudden shortness of breath (indicating a possible clot in the lung)
- Pain in the calf (indicating a possible clot in the leg)
- Crushing chest pain or heaviness in the chest (indicating a possible heart attack)
- Sudden severe headache or vomiting, dizziness or fainting, disturbances of vision or speech, weakness, or numbness in an arm or leg (indicating a possible stroke)
- Sudden partial or complete loss of vision (indicating a possible clot in the eye)
- Breast lumps (indicating possible breast cancer or fibrocystic disease of the breast; ask your doctor or healthcare provider to show you how to examine your breasts)
- Severe pain or tenderness in the stomach area (indicating a possibly ruptured liver tumor)
- Difficulty in sleeping, weakness, lack of energy, fatigue, or change in mood (possibly indicating severe depression)
- Jaundice or a yellowing of the skin or eyeballs, accompanied frequently by fever, fatigue, loss of appetite, dark colored urine, or light colored bowel movements (indicating possible liver problems)

SIDE EFFECTS OF ORAL CONTRACEPTIVES

1. Vaginal Bleeding
Irregular vaginal bleeding or spotting may occur while you are taking the pills. Irregular bleeding may vary from slight staining between menstrual periods to breakthrough bleeding which is a flow much like a regular period. Irregular bleeding occurs most often during the first few months of oral contraceptive use, but may also occur after you have been taking the pill for some time. Such bleeding may be temporary and usually does not indicate serious problems. It is important to continue taking your pills on schedule. If the bleeding occurs in more than one cycle or lasts for more than a few days, talk to your doctor or healthcare provider.

2. Contact Lenses
If you wear contact lenses and notice a change in vision or an inability to wear your lenses, contact your doctor or healthcare provider.

3. Fluid Retention
Oral contraceptives may cause edema (fluid retention) with swelling of the fingers or ankles and may raise your blood pressure. If you experience fluid retention, contact your doctor or healthcare provider.

4. Melasma
A spotty darkening of the skin is possible, particularly of the face.

5. Other Side Effects
Other side effects may include change in appetite, headache, nervousness, depression, dizziness, loss of scalp hair, rash, and vaginal infections.

If any of these side effects bother you, call your doctor or healthcare provider.

GENERAL PRECAUTIONS

1. Missed Periods and Use of Oral Contraceptives Before or During Early Pregnancy
There may be times when you may not menstruate regularly after you have completed taking a cycle of pills. If you have taken your pills regularly and miss one menstrual period, continue taking your pills for the next cycle but be sure to inform your healthcare provider before doing so. If you have not taken the pills daily as instructed and missed a menstrual period, or if you missed two consecutive menstrual periods, you may be pregnant. Check with your healthcare provider immediately to determine whether you are pregnant. Do not continue to take oral contraceptives until you are sure you are not pregnant, but continue to use another method of contraception.

There is no conclusive evidence that oral contraceptive use is associated with an increase in birth defects, when taken inadvertently during early pregnancy. Previously, a few studies had reported that oral contraceptives might be associated with birth defects, but these studies have not been confirmed. Nevertheless, oral contraceptives or any other drugs should not be used during pregnancy unless clearly necessary and prescribed by your doctor. You should check with your doctor about risks to your unborn child of any medication taken during pregnancy.

2. While Breastfeeding
If you are breastfeeding, consult your doctor before starting oral contraceptives. Some of the drug will be passed on to the child in the milk. A few adverse effects on the child have been reported, including yellowing of the skin (jaundice) and breast enlargement. In addition, oral contraceptives may decrease the amount and quality of your milk. If possible, do not use oral contraceptives while breastfeeding. You should use another method of contraception since breastfeeding provides only partial protection from becoming pregnant and this partial protection decreases significantly as you breastfeed for longer periods of time. You should consider starting oral contraceptives only after you have weaned your child completely.

3. Laboratory Tests
If you are scheduled for any laboratory tests, tell your doctor you are taking birth control pills. Certain blood tests may be affected by birth control pills.

4. Drug Interactions
Certain drugs may interact with birth control pills to make them less effective in preventing pregnancy or cause an increase in breakthrough bleeding. Such drugs include rifampin; drugs used for epilepsy such as barbiturates (for example, phenobarbital), carbamazepine, and phenytoin (Dilantin® is one brand of this drug); troglitazone; phenylbutazone; and possibly certain antibiotics. You may need to use additional contraception when you take drugs which can make oral contraceptives less effective.

Birth control pills interact with certain drugs. These drugs include acetaminophen, clofibric acid, cyclosporine, morphine, prednisolone, salicylic acid, temazepam, and theophylline. You should tell your doctor if you are taking any of these medications.

5. This product (like all oral contraceptives) is intended to prevent pregnancy. It does not protect against transmission of HIV (AIDS) and other sexually transmitted diseases such as Chlamydia, genital herpes, genital warts, gonorrhea, hepatitis B, and syphilis.

INSTRUCTIONS TO PATIENT

TABLET DISPENSER

The MICROGESTIN tablet dispenser has been designed to make oral contraceptive dosing as easy and as convenient as possible. The tablets are arranged in either three or four rows of seven tablets each, with the days of the week appearing above the first row of tablets.

If your TABLET DISPENSER contains: | You are taking:
21 white tablets | MICROGESTIN 1/20
21 green tablets | MICROGESTIN 1.5/30
21 white tablets and 7 brown tablets | MICROGESTIN Fe 1/20
21 green tablets and 7 brown tablets | MICROGESTIN Fe 1.5/30

Each white tablet contains 1 mg norethindrone acetate and 20 mcg ethinyl estradiol.
Each green tablet contains 1.5 mg norethindrone acetate and 30 mcg ethinyl estradiol.
Each brown tablet contains 75 mg ferrous fumarate, and is intended to help you remember to take the tablets correctly. These brown tablets are not intended to have any health benefit.

DIRECTIONS

To remove a tablet, press down on it with your thumb or finger. The tablet will drop through the back of the tablet dispenser. Do not press with your thumbnail, fingernail, or any other sharp object.

HOW TO TAKE THE PILL

IMPORTANT POINTS TO REMEMBER

BEFORE YOU START TAKING YOUR PILLS:

1. BE SURE TO READ THESE DIRECTIONS:
Before you start taking your pills.
Anytime you are not sure what to do.

2. THE RIGHT WAY TO TAKE THE PILL IS TO TAKE ONE PILL EVERY DAY AT THE SAME TIME. If you miss pills you could get pregnant. This includes starting the pack late. The more pills you miss, the more likely you are to get pregnant.

3. MANY WOMEN HAVE SPOTTING OR LIGHT BLEEDING, OR MAY FEEL SICK TO THEIR STOMACH DURING THE FIRST 1-3 PACKS OF PILLS. If you do have spotting or light bleeding or feel sick to your stomach, do not stop taking the pill. The problem will usually go away. If it doesn’t go away, check with your doctor or clinic.

4. MISSING PILLS CAN ALSO CAUSE SPOTTING OR LIGHT BLEEDING, even when you make up these missed pills. On the days you take 2 pills to make up for missed pills, you could also feel a little sick to your stomach.

5. IF YOU HAVE VOMITING OR DIARRHEA, for any reason, or IF YOU TAKE SOME MEDICINES, including some antibiotics, your birth control pills may not work as well. Use a back-up birth control method (such as condoms or foam) until you check with your doctor or clinic.

6. IF YOU HAVE TROUBLE REMEMBERING TO TAKE THE PILL, talk to your doctor or clinic about how to make pill-taking easier or about using another method of birth control.

7. IF YOU HAVE ANY QUESTIONS OR ARE UNSURE ABOUT THE INFORMATION IN THIS LEAFLET, call your doctor or clinic.

BEFORE YOU START TAKING YOUR PILLS

1. DECIDE WHAT TIME OF DAY YOU WANT TO TAKE YOUR PILL. It is important to take it at about the same time every day.

2. LOOK AT YOUR PILL PACK TO SEE IF IT HAS 21 OR 28 PILLS:
The 21-Day pill pack has 21 "active" white or green pills (with hormones) to take for 3 weeks, followed by 1 week without pills.
The 28-Day pill pack has 21 "active" white or green pills (with hormones) to take for 3 weeks, followed by 1 week of reminder brown pills (without hormones).

3. ALSO FIND:
1) where on the pack to start taking pills,
2) in what order to take the pills (follow the arrows), and
3) the week numbers as shown in the following pictures:

MICROGESTIN 1/20 will contain: ALL WHITE PILLS.
MICROGESTIN 1.5/30 will contain: ALL GREEN PILLS.

MICROGESTIN Fe 1/20 will contain: 21 WHITE PILLS for WEEKS 1, 2, and 3.
WEEK 4 will contain BROWN PILLS ONLY.

MICROGESTIN Fe 1.5/30 will contain: 21 GREEN PILLS for WEEKS 1, 2, and 3.
WEEK 4 will contain BROWN PILLS ONLY.

4. BE SURE YOU HAVE READY AT ALL TIMES:
ANOTHER KIND OF BIRTH CONTROL (such as condoms or foam) to use as a back-up in case you miss pills.
An EXTRA, FULL PILL PACK.

WHEN TO START THE FIRST PACK OF PILLS

You have a choice of which day to start taking your first pack of pills. Decide with your doctor or clinic which is the best day for you. Pick a time of day which will be easy to remember.

DAY-1 START:

1. Pick the day label strip that starts with the first day of your period. (This is the day you start bleeding or spotting, even if it is almost midnight when the bleeding begins.)

2. Place this day label strip on the tablet dispenser over the area that has the days of the week (starting with Sunday) printed on the plastic.

3. Take the first "active" white or green pill of the first pack during the first 24 hours of your period.

4. You will not need to use a back-up method of birth control, since you are starting the pill at the beginning of your period.

SUNDAY START:

1. Take the first "active" white or green pill of the first pack on the Sunday after your period starts, even if you are still bleeding. If your period begins on Sunday, start the pack that same day.

2. Use another method of birth control as a back-up method if you have sex anytime from the Sunday you start your first pack until the next Sunday (7 days). Condoms or foam are good back-up methods of birth control.

WHAT TO DO DURING THE MONTH

1. TAKE ONE PILL AT THE SAME TIME EVERY DAY UNTIL THE PACK IS EMPTY.
Do not skip pills even if you are spotting or bleeding between monthly periods or feel sick to your stomach (nausea).
Do not skip pills even if you do not have sex very often.

2. WHEN YOU FINISH A PACK OR SWITCH YOUR BRAND OF PILLS:
21 pills: Wait 7 days to start the next pack. You will probably have your period during that week. Be sure that no more than 7 days pass between 21-day packs.
28 pills: Start the next pack on the day after your last “reminder” pill. Do not wait any days between packs.

WHAT TO DO IF YOU MISS PILLS

If you MISS 1 white or green "active" pill:

1. Take it as soon as you remember. Take the next pill at your regular time. This means you may take 2 pills in 1 day.

2. You do not need to use a back-up birth control method if you have sex.

If you MISS 2 white or green "active" pills in a row in WEEK 1 OR WEEK 2 of your pack:

1. Take 2 pills on the day you remember and 2 pills the next day.

2. Then take 1 pill a day until you finish the pack.

3. You COULD GET PREGNANT if you have sex in the 7 days after you miss pills. You MUST use another birth control method (such as condoms or foam) as a back-up method of birth control until you have taken a white or green "active" pill every day for 7 days.

If you MISS 2 white or green "active" pills in a row in THE 3rd WEEK:

1. If you are a Day-1 Starter:
THROW OUT the rest of the pill pack and start a new pack that same day.
If you are a Sunday Starter:
Keep taking 1 pill every day until Sunday. On Sunday, THROW OUT the rest of the pack and start a new pack of pills that same day.

2. You may not have your period this month, but this is expected. However, if you miss your period 2 months in a row, call your doctor or clinic because you might be pregnant.

3. You COULD GET PREGNANT if you have sex in the 7 days after you miss pills. You MUST use another birth control method (such as condoms or foam) as a back-up method of birth control until you have taken a white or green "active" pill every day for 7 days.

If you MISS 3 OR MORE white or green "active" pills in a row (during the first 3 weeks):

1. If you are a Day-1 Starter:
THROW OUT the rest of the pill pack and start a new pack that same day.
If you are a Sunday Starter:
Keep taking 1 pill every day until Sunday. On Sunday, THROW OUT the rest of the pack and start a new pack of pills that same day.

2. You may not have your period this month, but this is expected. However, if you miss your period 2 months in a row, call your doctor or clinic because you might be pregnant.

3. You COULD GET PREGNANT if you have sex in the 7 days after you miss pills. You MUST use another birth control method (such as condoms or foam) as a back-up method of birth control until you have taken a white or green "active" pill every day for 7 days.

A REMINDER FOR THOSE ON 28-DAY PACKS:
IF YOU FORGET ANY OF THE 7 BROWN "REMINDER" PILLS IN WEEK 4:
THROW AWAY THE PILLS YOU MISSED.
KEEP TAKING 1 PILL EACH DAY UNTIL THE PACK IS EMPTY.
YOU DO NOT NEED A BACK-UP METHOD.
FINALLY, IF YOU ARE STILL NOT SURE WHAT TO DO ABOUT THE PILLS YOU HAVE MISSED:
Use a BACK-UP METHOD anytime you have sex.
KEEP TAKING ONE WHITE OR GREEN "ACTIVE" PILL EACH DAY until you can reach your doctor or clinic.

PREGNANCY DUE TO PILL FAILURE

The incidence of pill failure resulting in pregnancy is approximately 1% (i.e., one pregnancy per 100 women per year) if taken every day as directed, but more typical failure rates are about 3%. If failure does occur, the risk to the fetus is minimal.

PREGNANCY AFTER STOPPING THE PILL

There may be some delay in becoming pregnant after you stop using oral contraceptives, especially if you had irregular menstrual cycles before you used oral contraceptives. It may be advisable to postpone conception until you begin menstruating regularly once you have stopped taking the pill and desire pregnancy.

There does not appear to be any increase in birth defects in newborn babies when pregnancy occurs soon after stopping the pill.

OVERDOSAGE

Serious ill effects have not been reported following ingestion of large doses of oral contraceptives by young children. Overdosage may cause nausea and withdrawal bleeding in females. In case of overdosage, contact your healthcare provider or pharmacist.

OTHER INFORMATION

Your healthcare provider will take a medical and family history and examine you before prescribing oral contraceptives. The physical examination may be delayed to another time if you request it and your healthcare provider believes that it is a good medical practice to postpone it. You should be reexamined at least once a year. Be sure to inform your healthcare provider if there is a family history of any of the conditions listed previously in this leaflet. Be sure to keep all appointments with your healthcare provider, because this is a time to determine if there are early signs of side effects of oral contraceptive use.

Do not use the drug for any condition other than the one for which it was prescribed. This drug has been prescribed specifically for you; do not give it to others who may want birth control pills.

HEALTH BENEFITS FROM ORAL CONTRACEPTIVES

In addition to preventing pregnancy, use of oral contraceptives may provide certain benefits. They are:

- Menstrual cycles may become more regular
- Blood flow during menstruation may be lighter and less iron may be lost. Therefore, anemia due to iron deficiency is less likely to occur
- Pain or other symptoms during menstruation may be encountered less frequently
- Ectopic (tubal) pregnancy may occur less frequently
- Noncancerous cysts or lumps in the breast may occur less frequently
- Acute pelvic inflammatory disease may occur less frequently
- Oral contraceptive use may provide some protection against developing two forms of cancer: cancer of the ovaries and cancer of the lining of the uterus.

If you want more information about birth control pills, ask your doctor or pharmacist. They have a more technical leaflet called the “Physician Insert,” which you may wish to read.

Remembering to take tablets according to schedule is stressed because of its importance in providing you the greatest degree of protection.

MISSED MENSTRUAL PERIODS FOR BOTH DOSAGE REGIMENS

At times there may be no menstrual period after a cycle of pills. Therefore, if you miss one menstrual period but have taken the pills exactly as you were supposed to, continue as usual into the next cycle. If you have not taken the pills correctly and miss a menstrual period, you may be pregnant and should stop taking oral contraceptives until your doctor or healthcare provider determines whether or not you are pregnant. Until you can get to your doctor or healthcare provider, use another form of contraception. If two consecutive menstrual periods are missed, you should stop taking pills until it is determined whether or not you are pregnant. Although there does not appear to be any increase in birth defects in newborn babies if you become pregnant while using oral contraceptives, you should discuss the situation with your doctor or healthcare provider.

Periodic Examination

Your doctor or healthcare provider will take a complete medical and family history before prescribing oral contraceptives. At that time and about once a year thereafter, he or she will generally examine your blood pressure, breasts, abdomen, and pelvic organs (including a Papanicolaou smear, i.e., test for cancer).

Keep this and all drugs out of the reach of children.

Rx only

Store below 30° C (86° F).

Distributed by:
Mayne Pharma
Greenville, NC 27834

MICROGESTIN® is a registered trademark of Mayne Pharma LLC.

Revised: June 2020

MICDPL-001